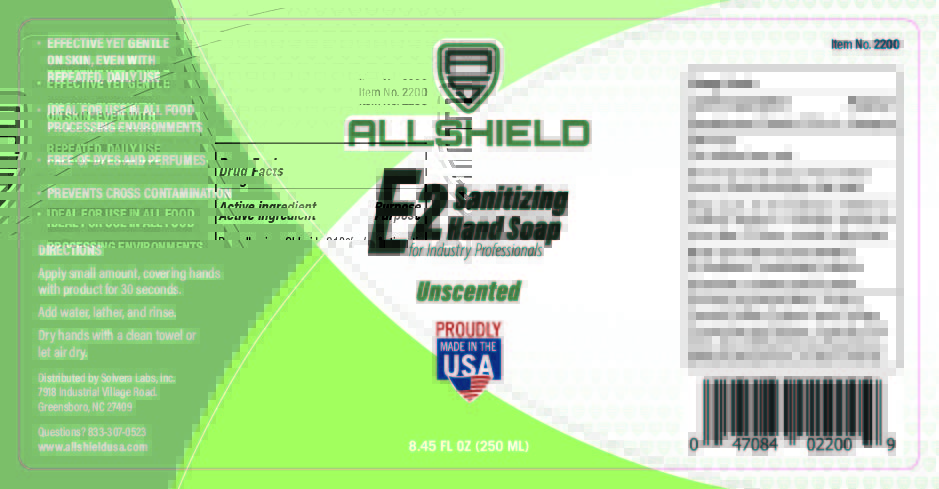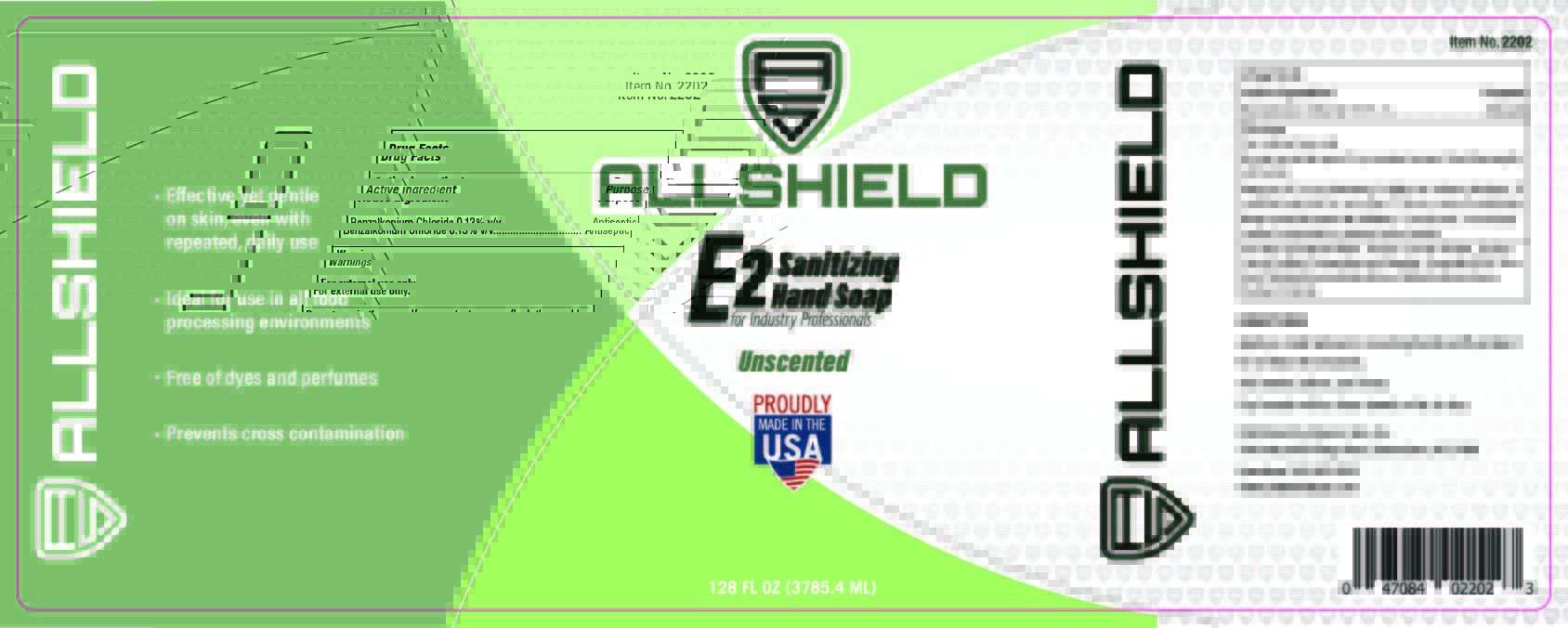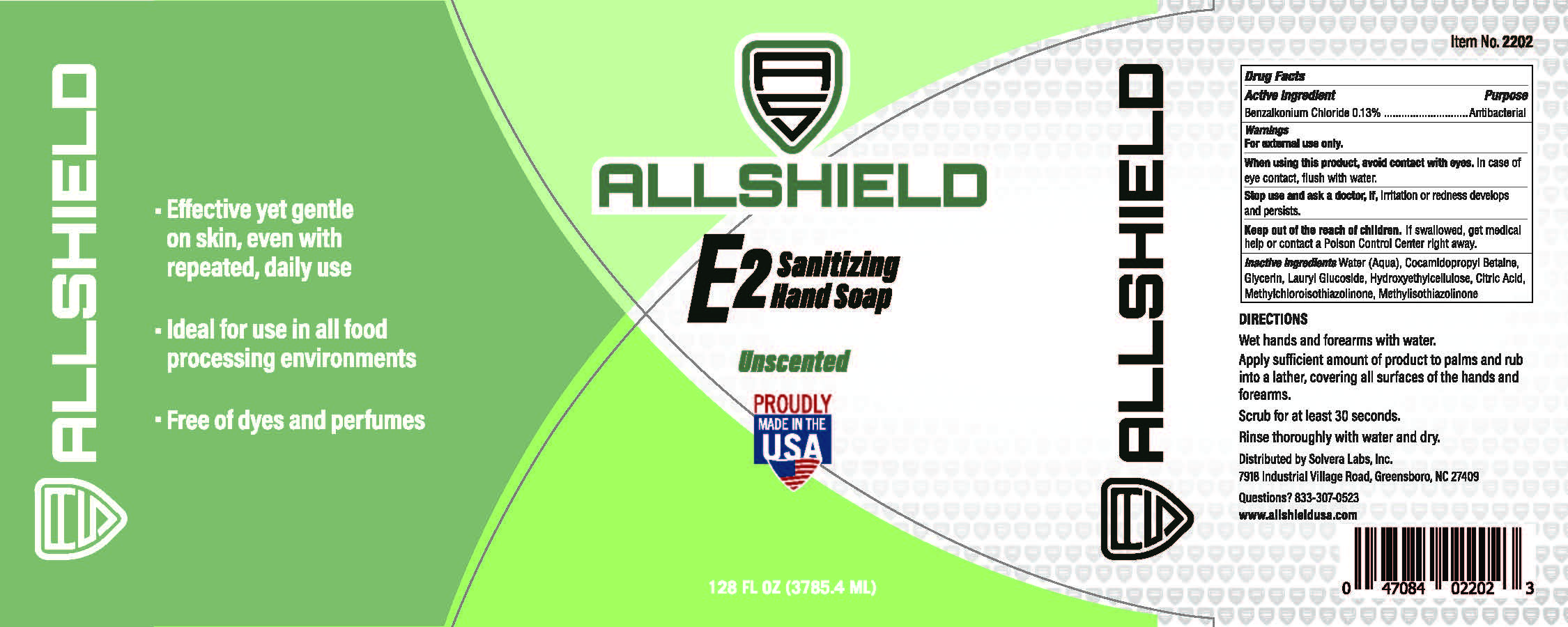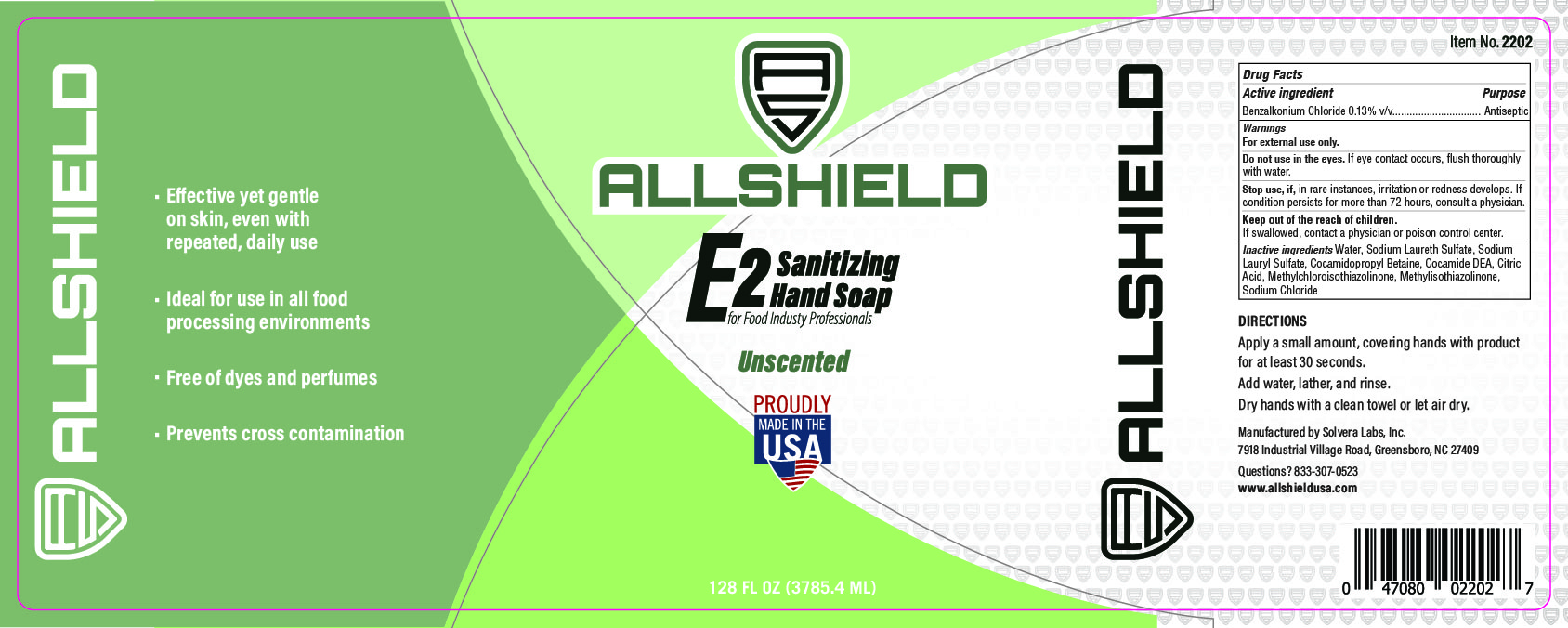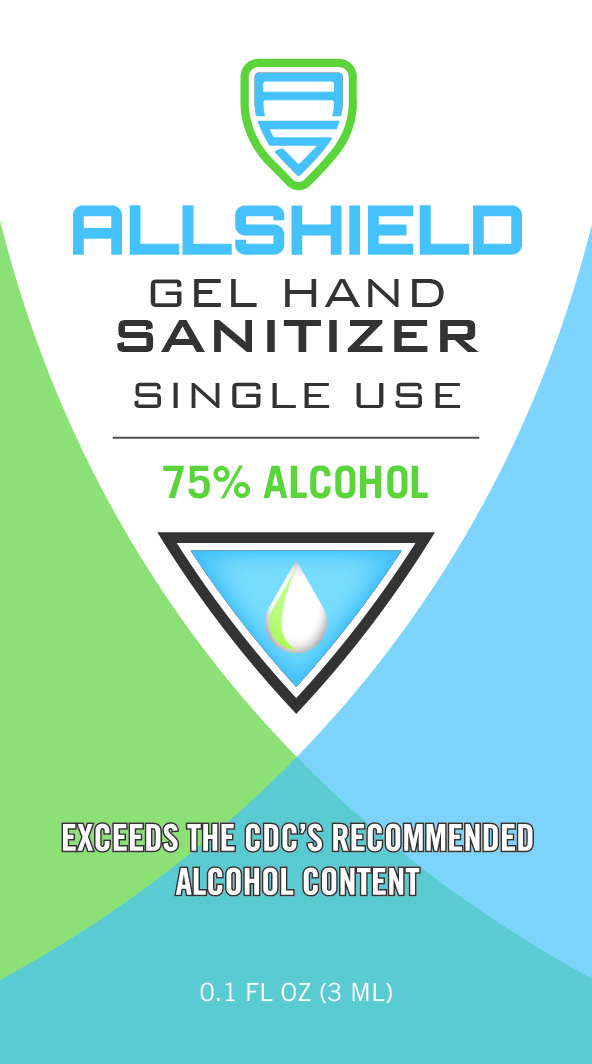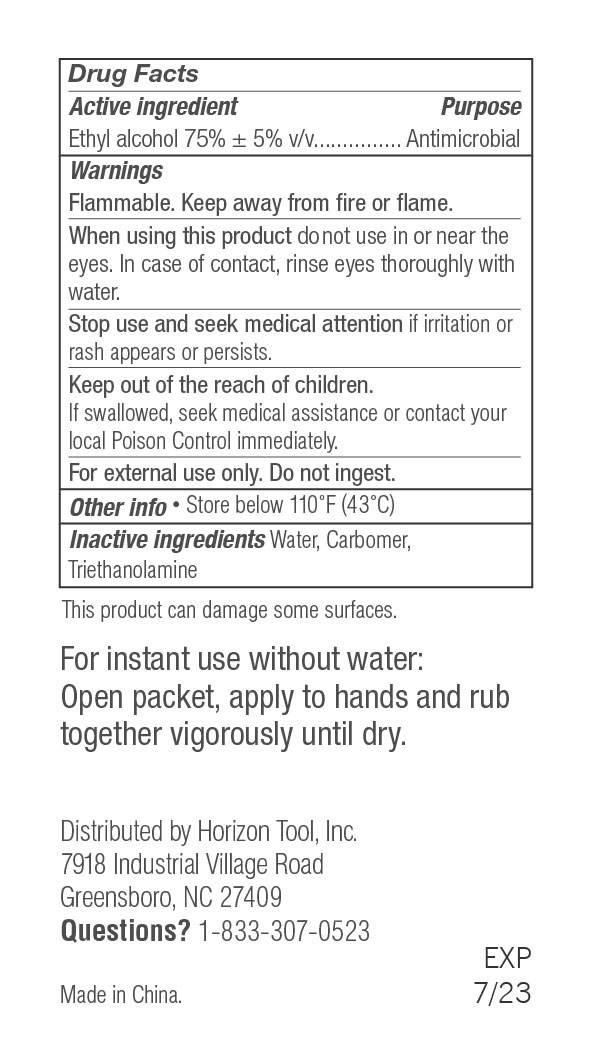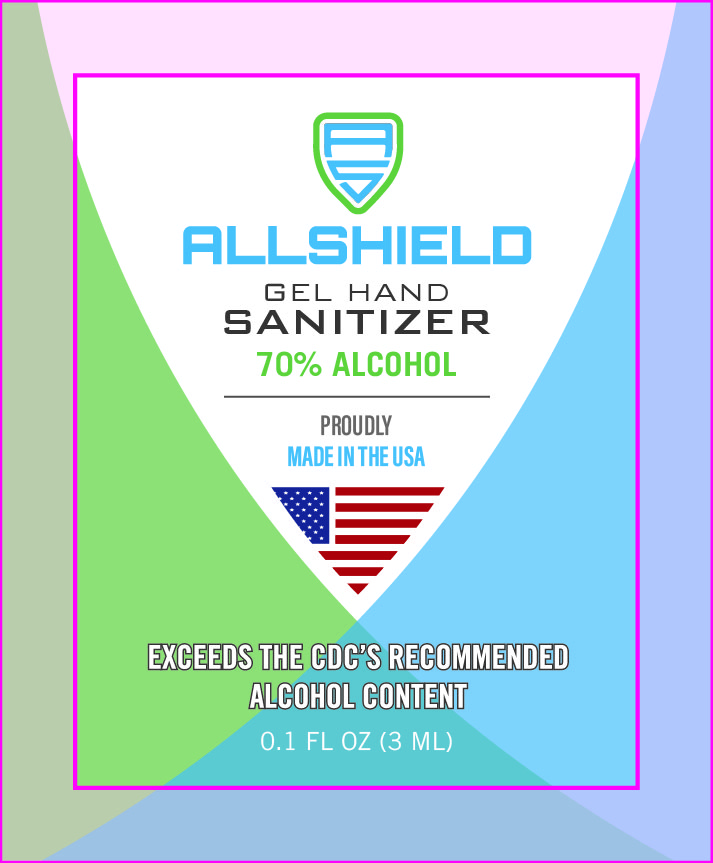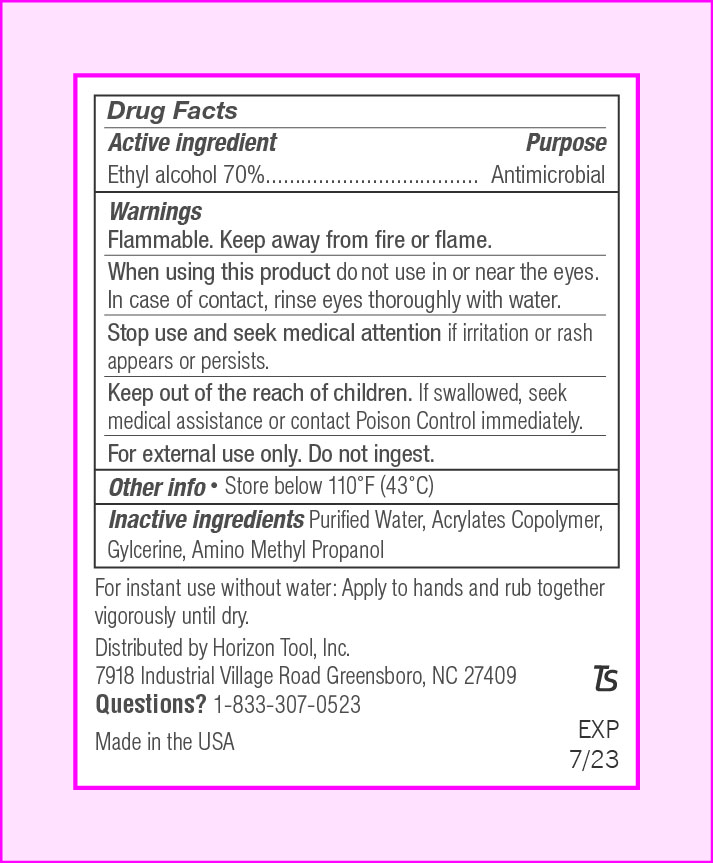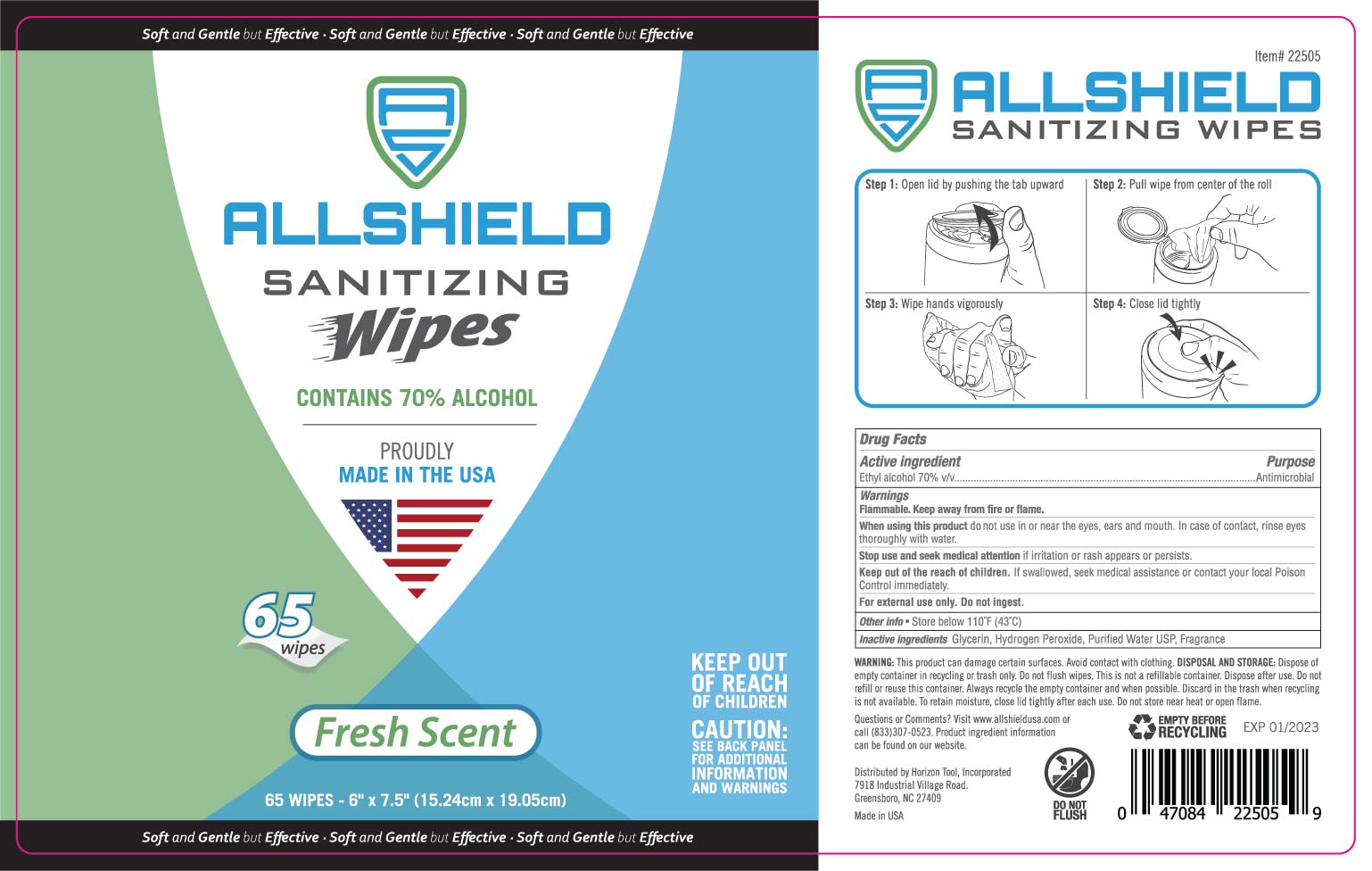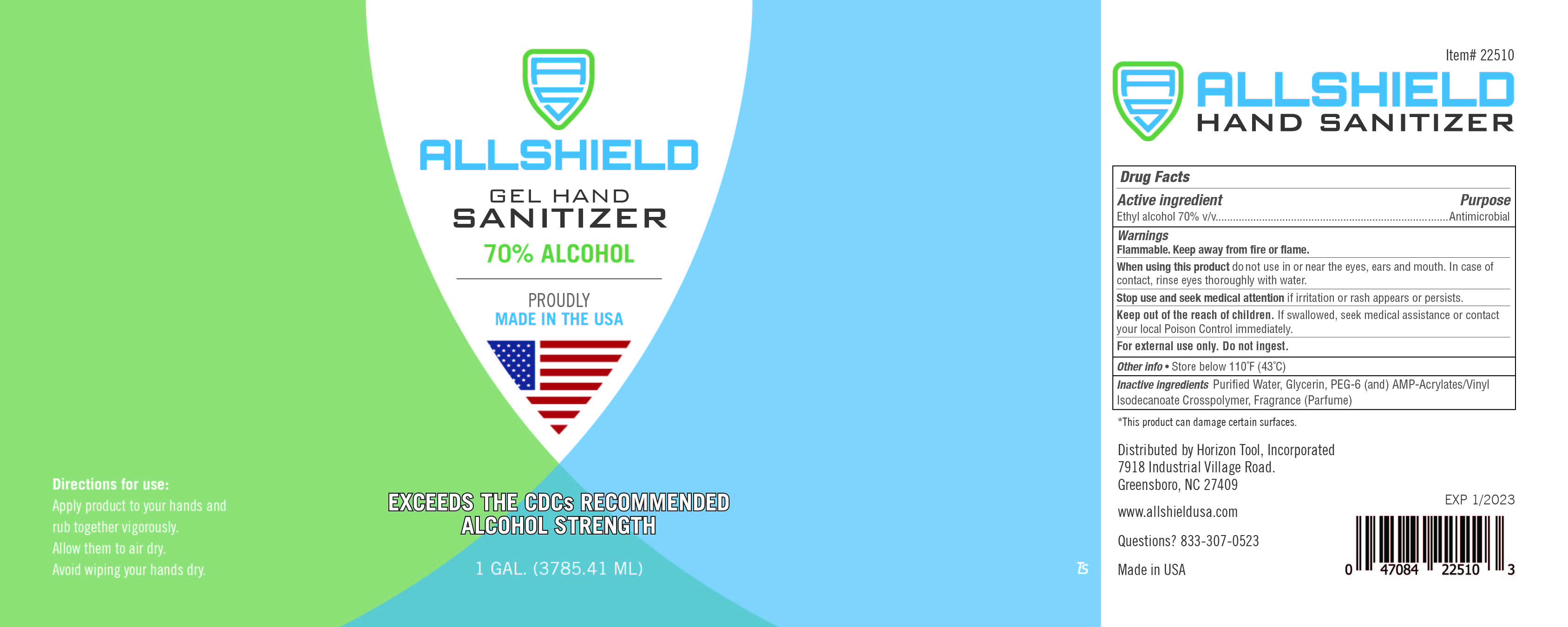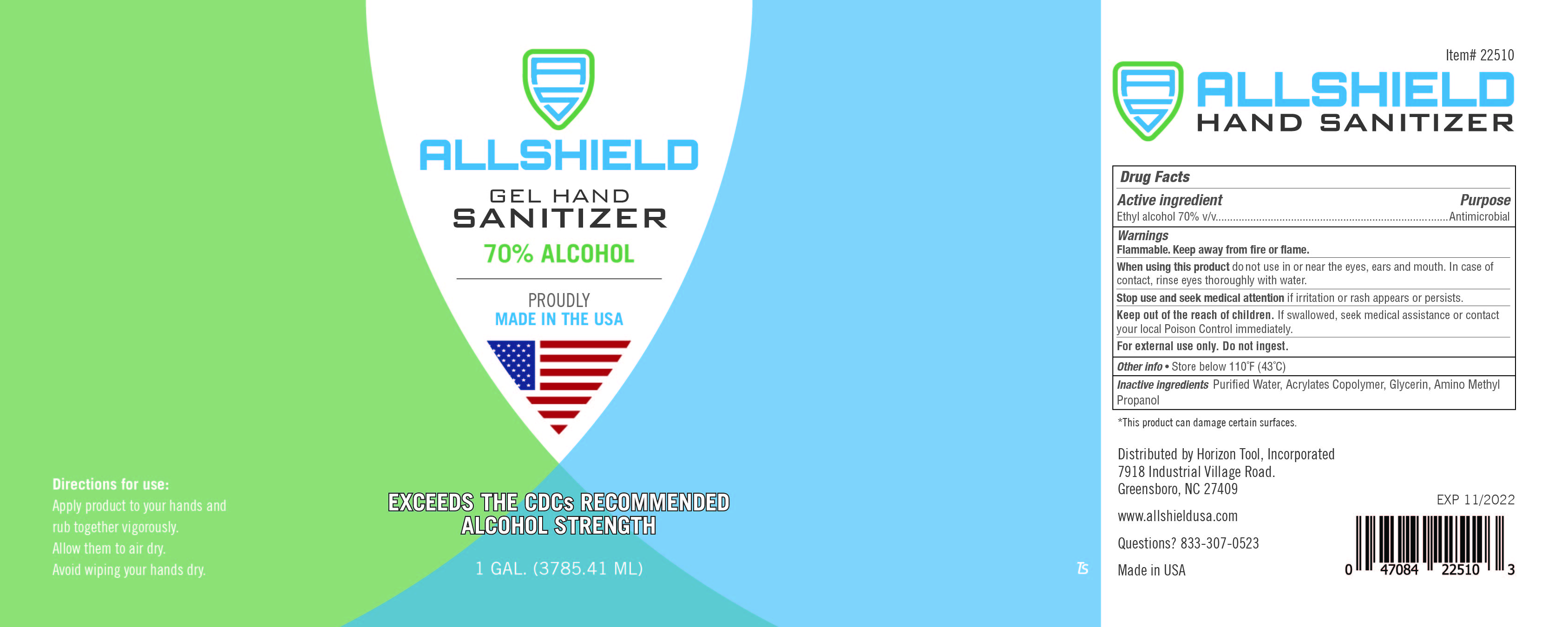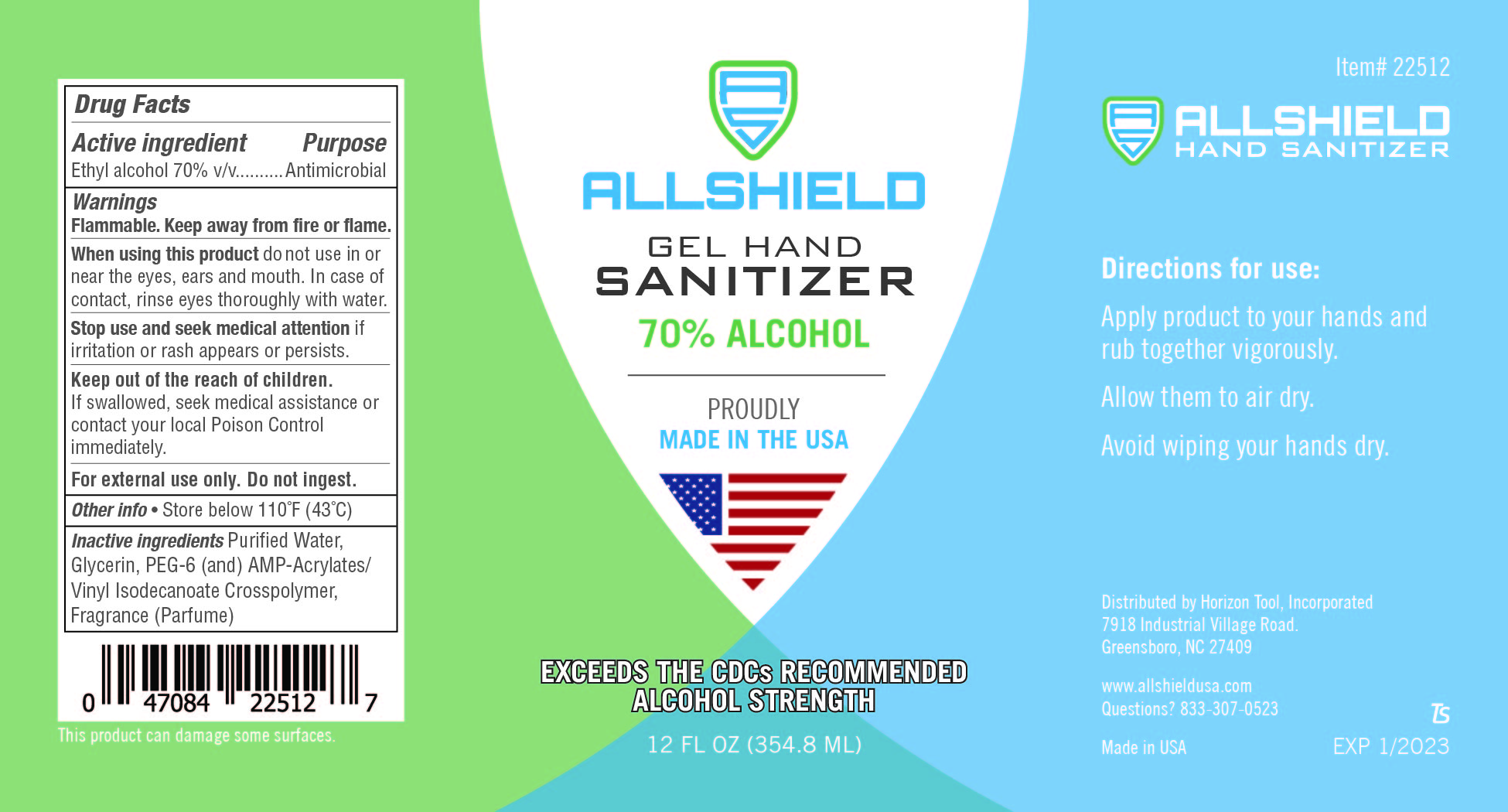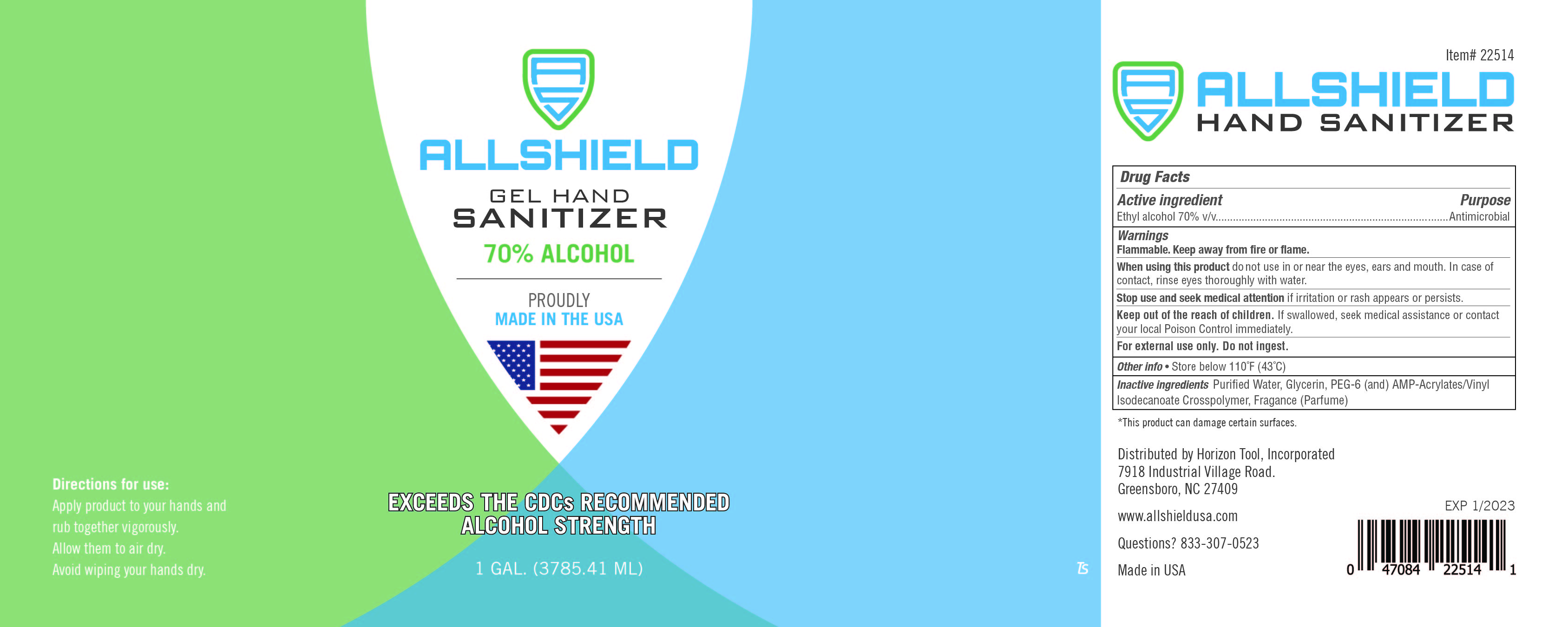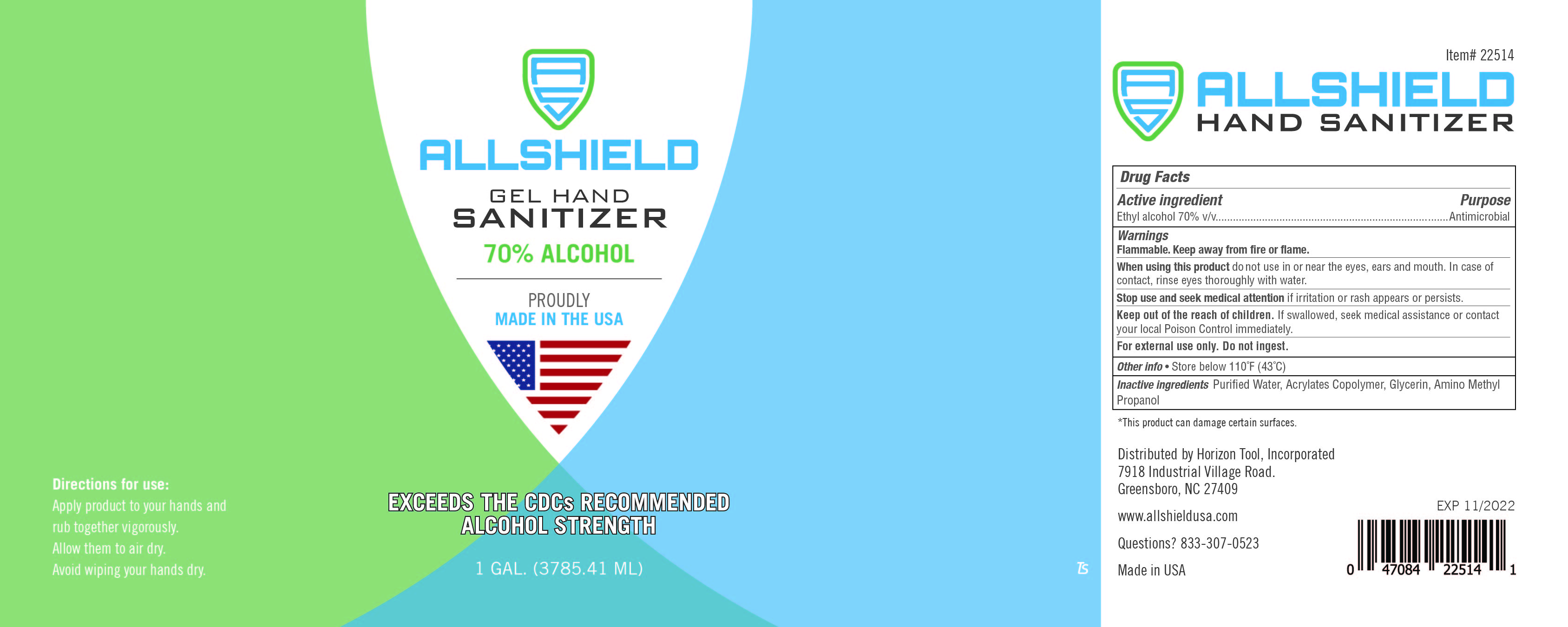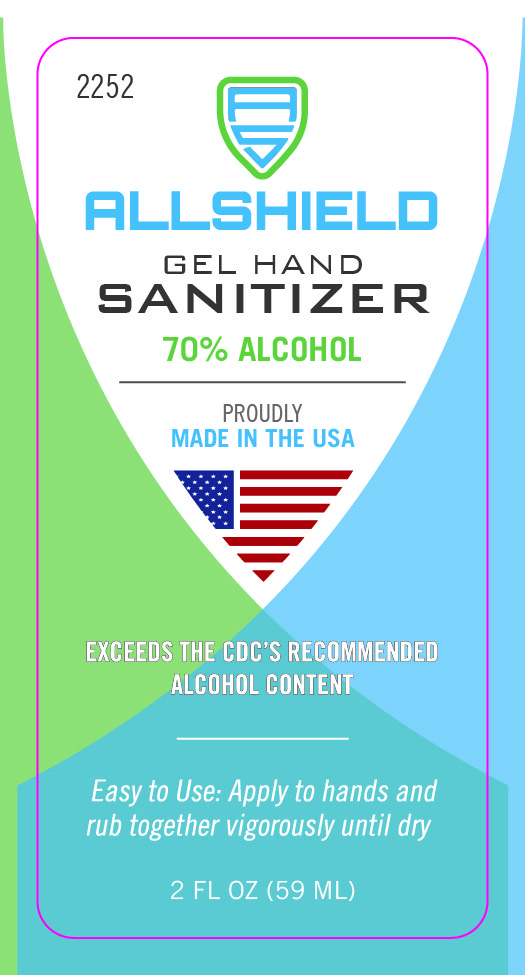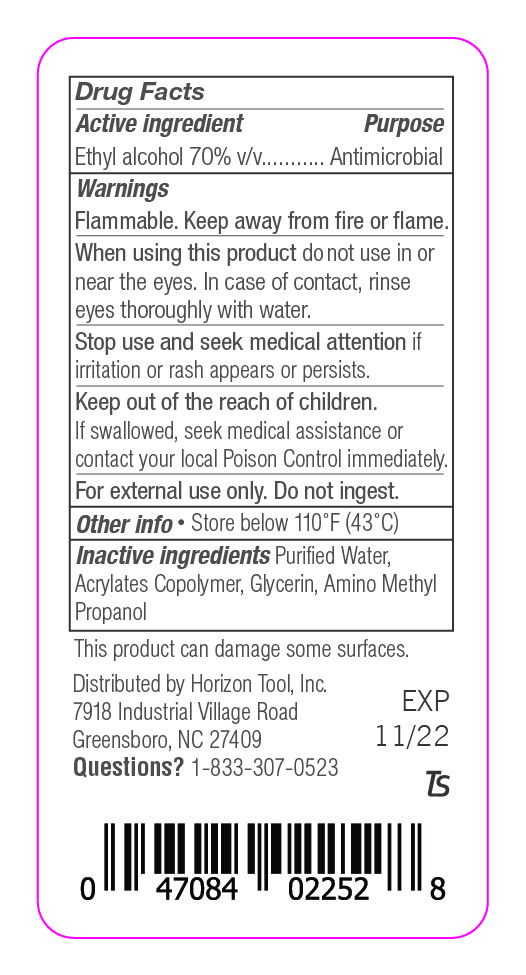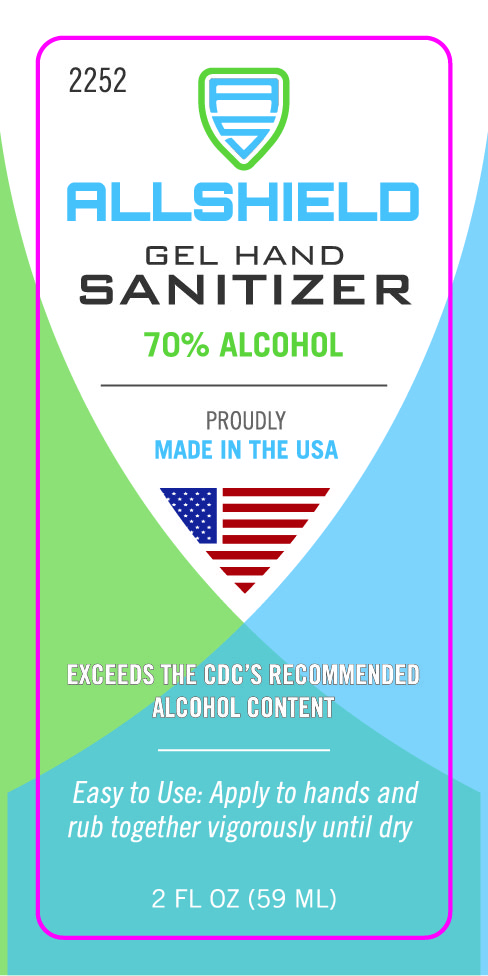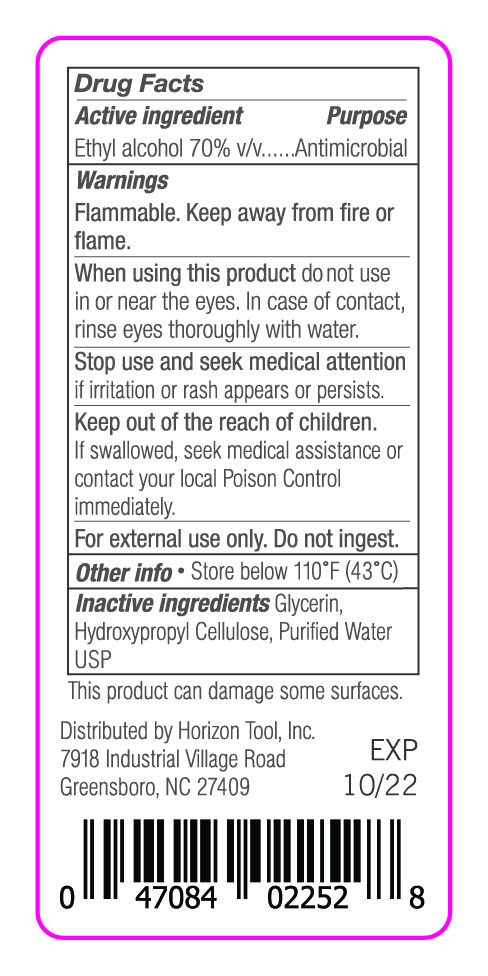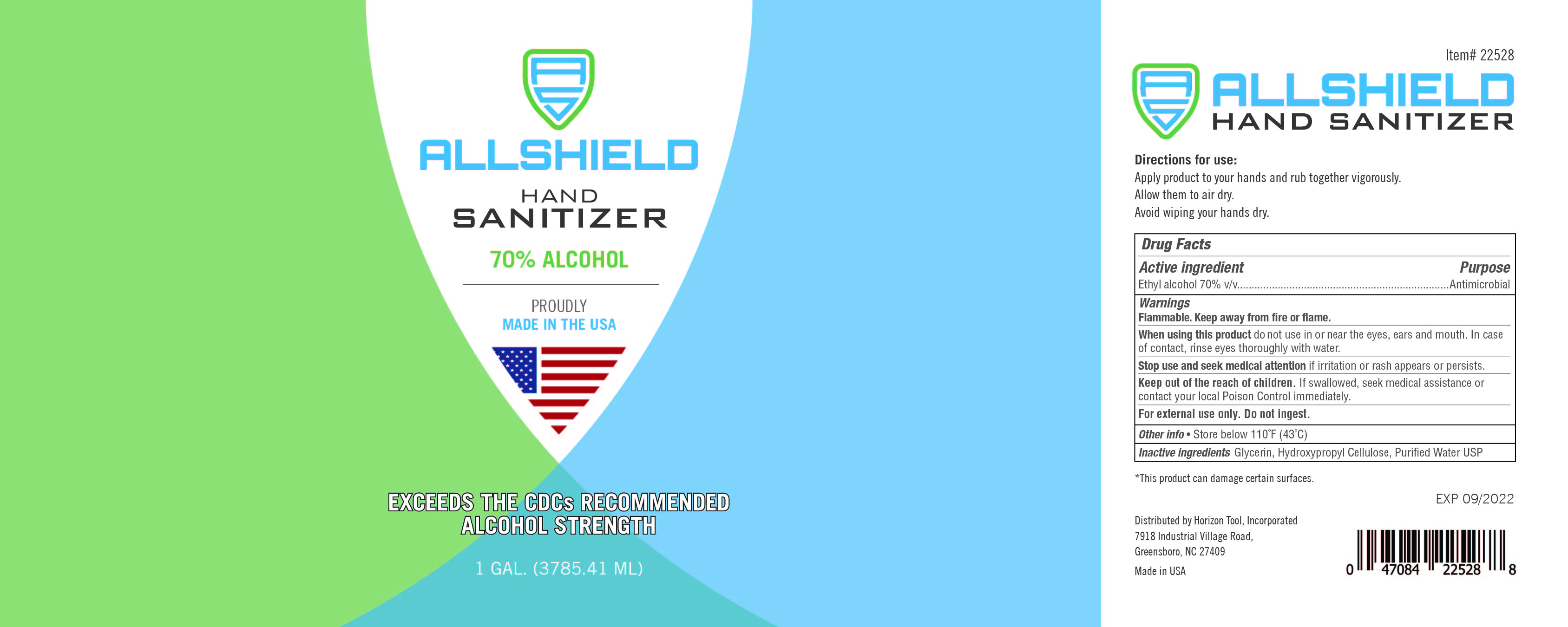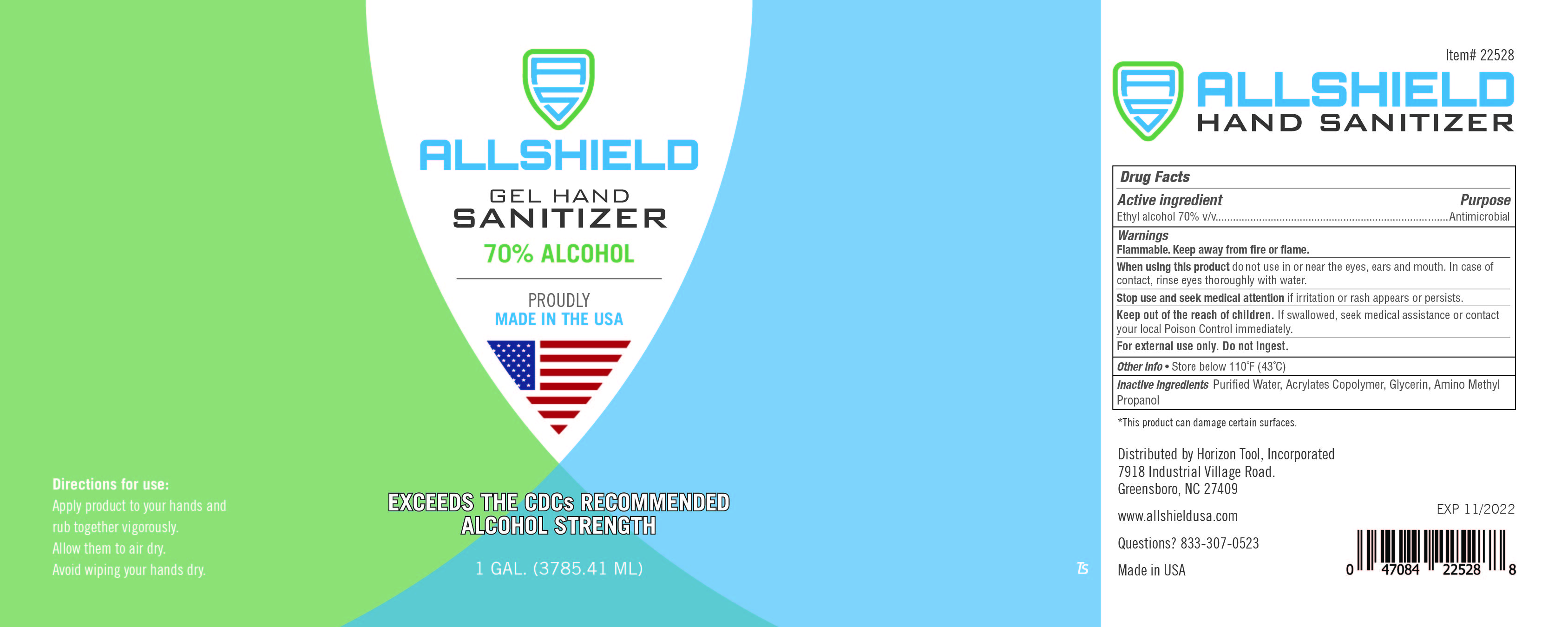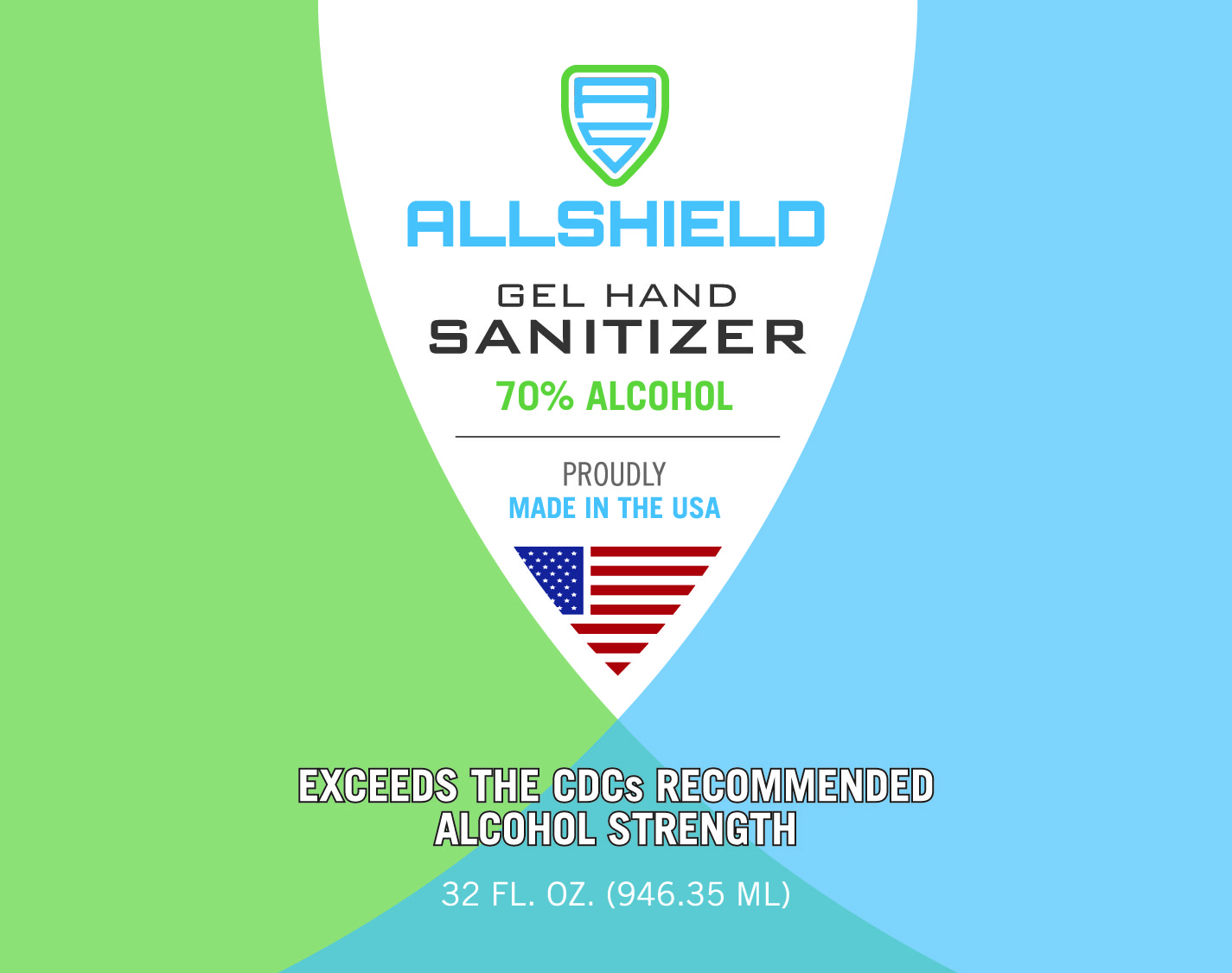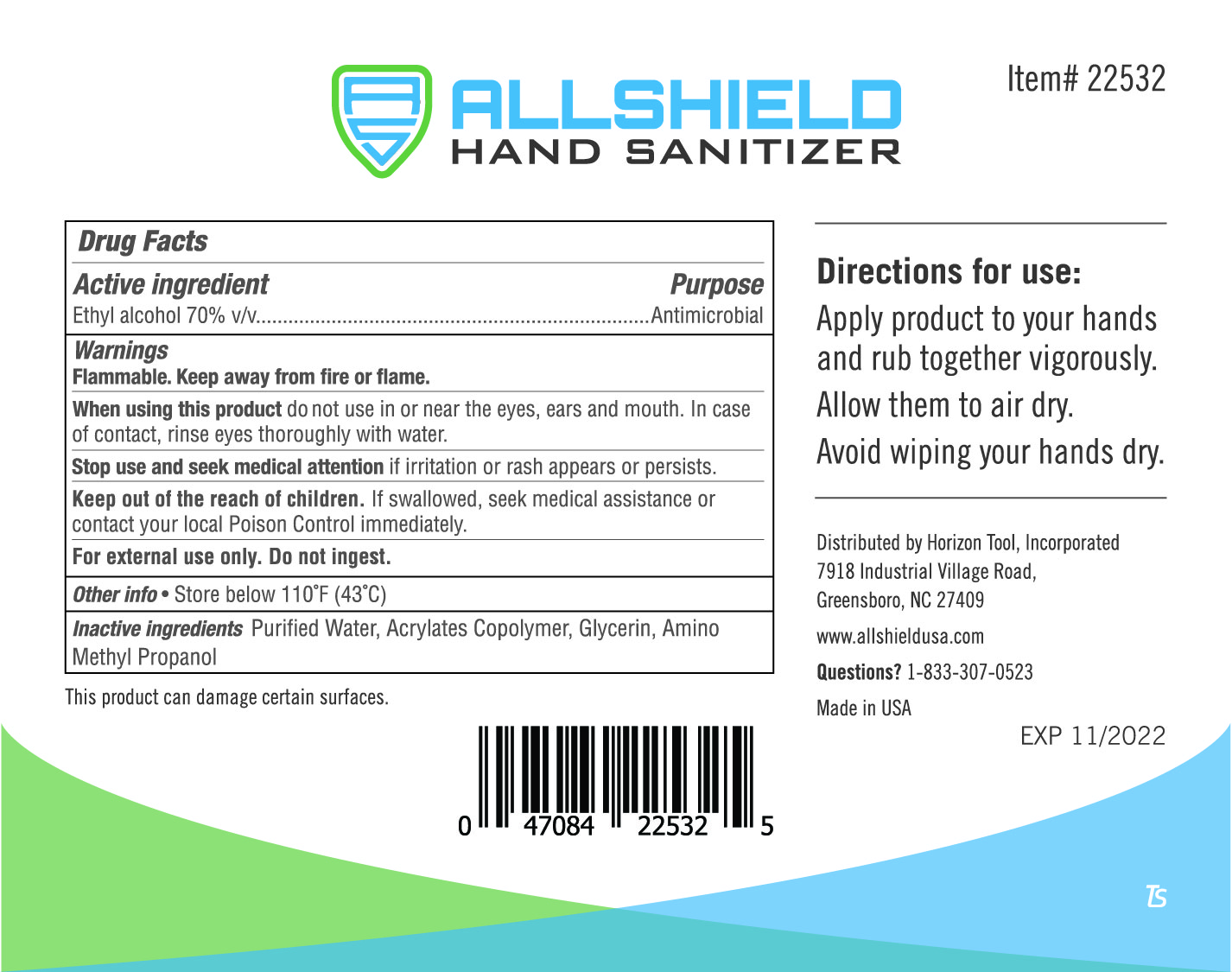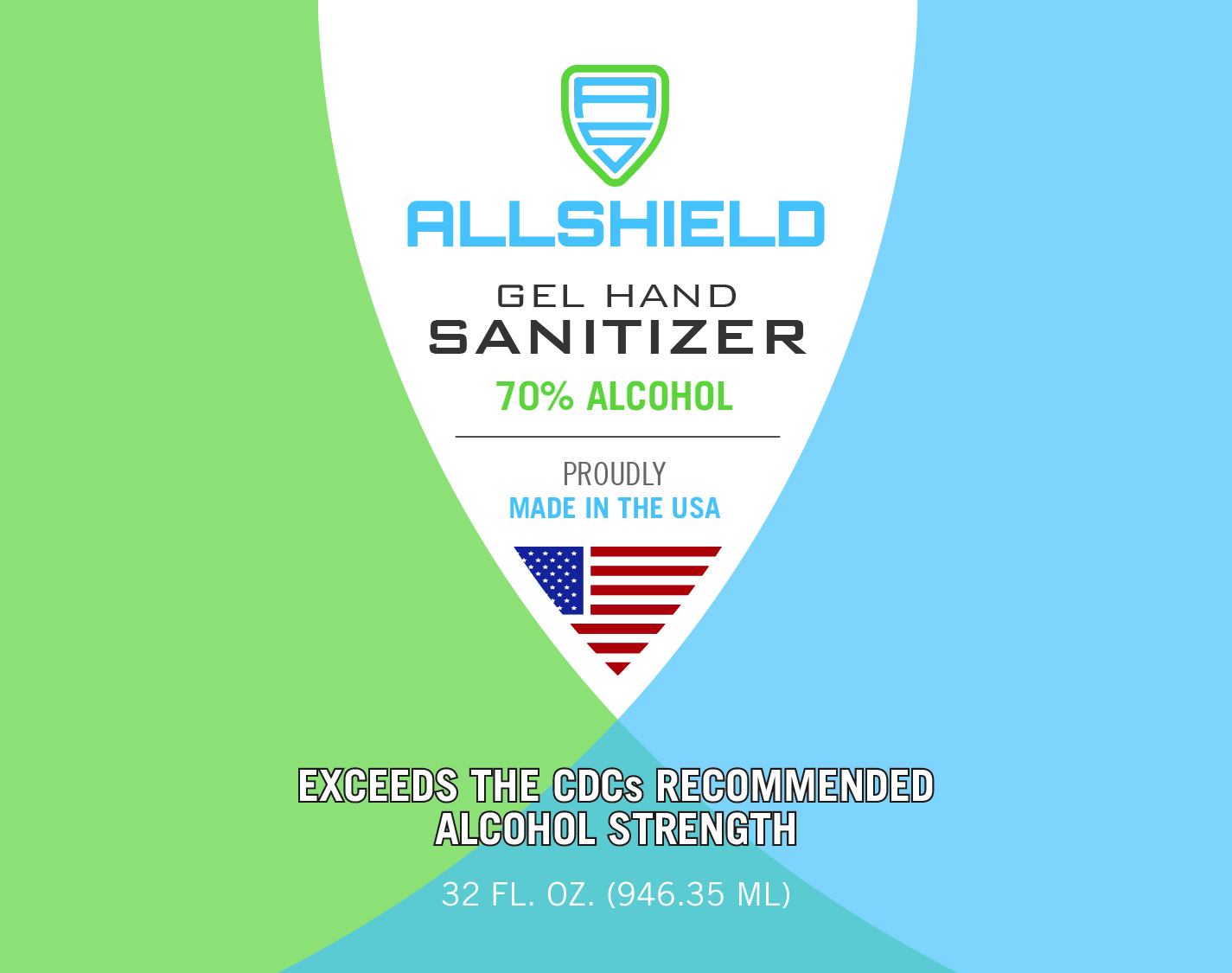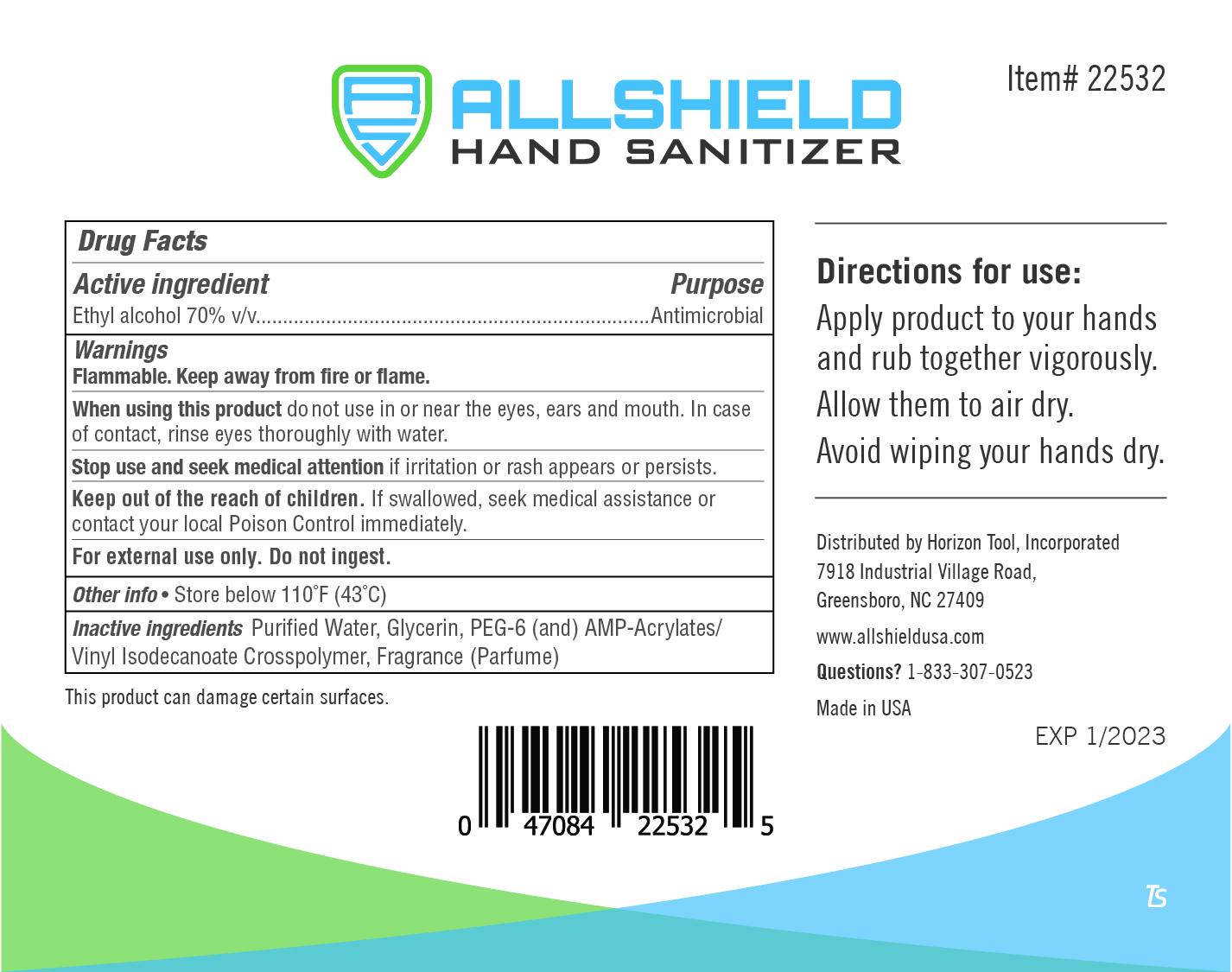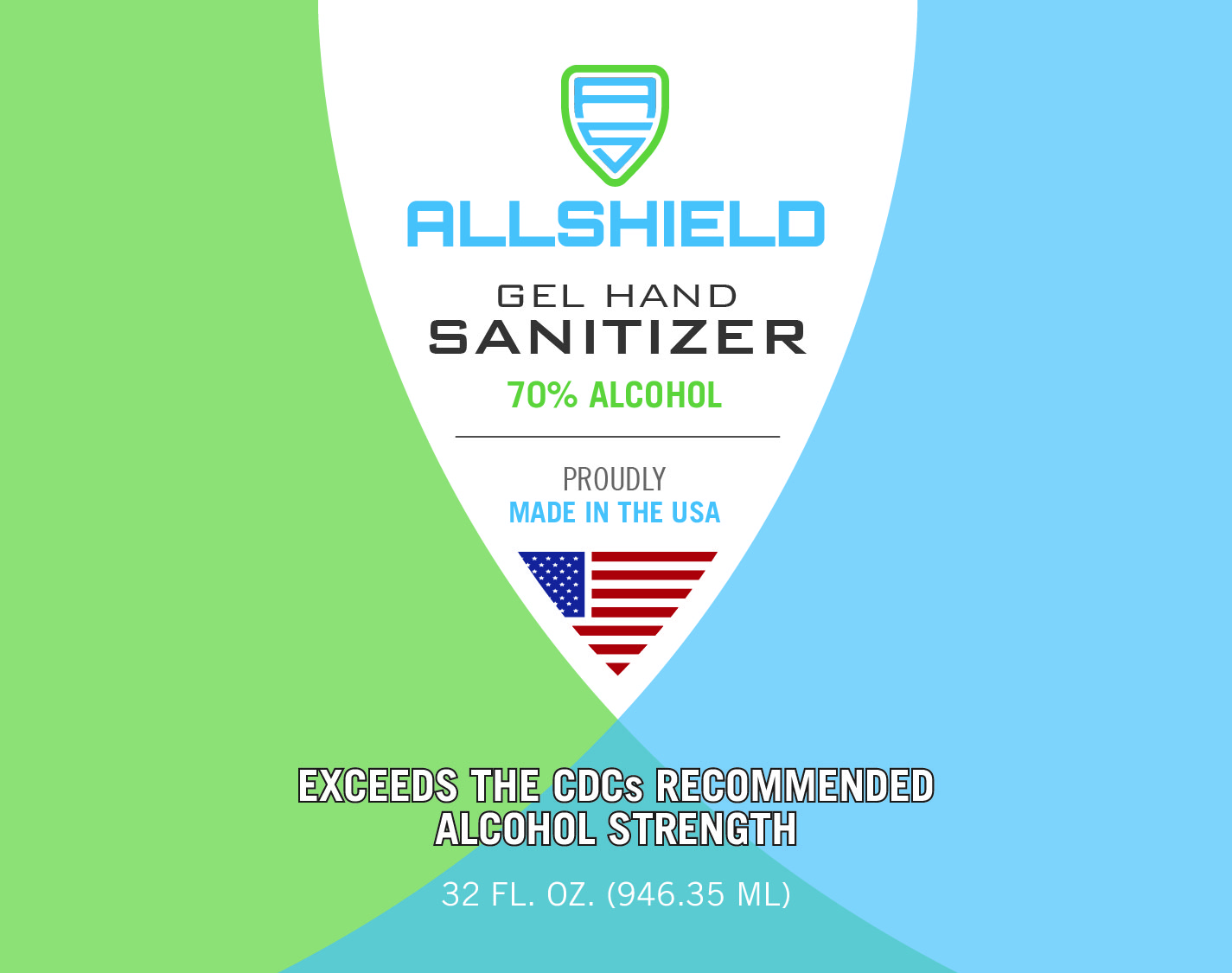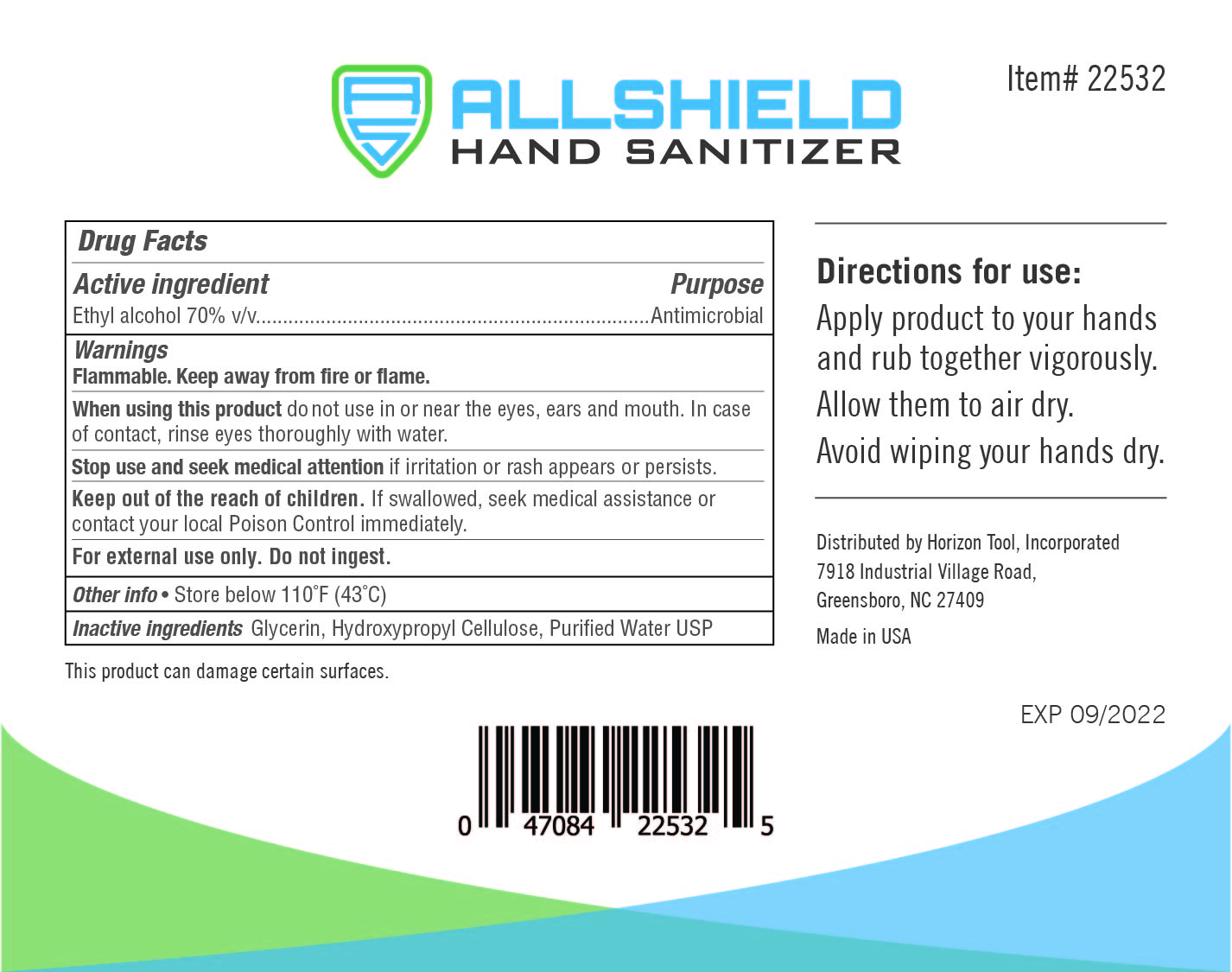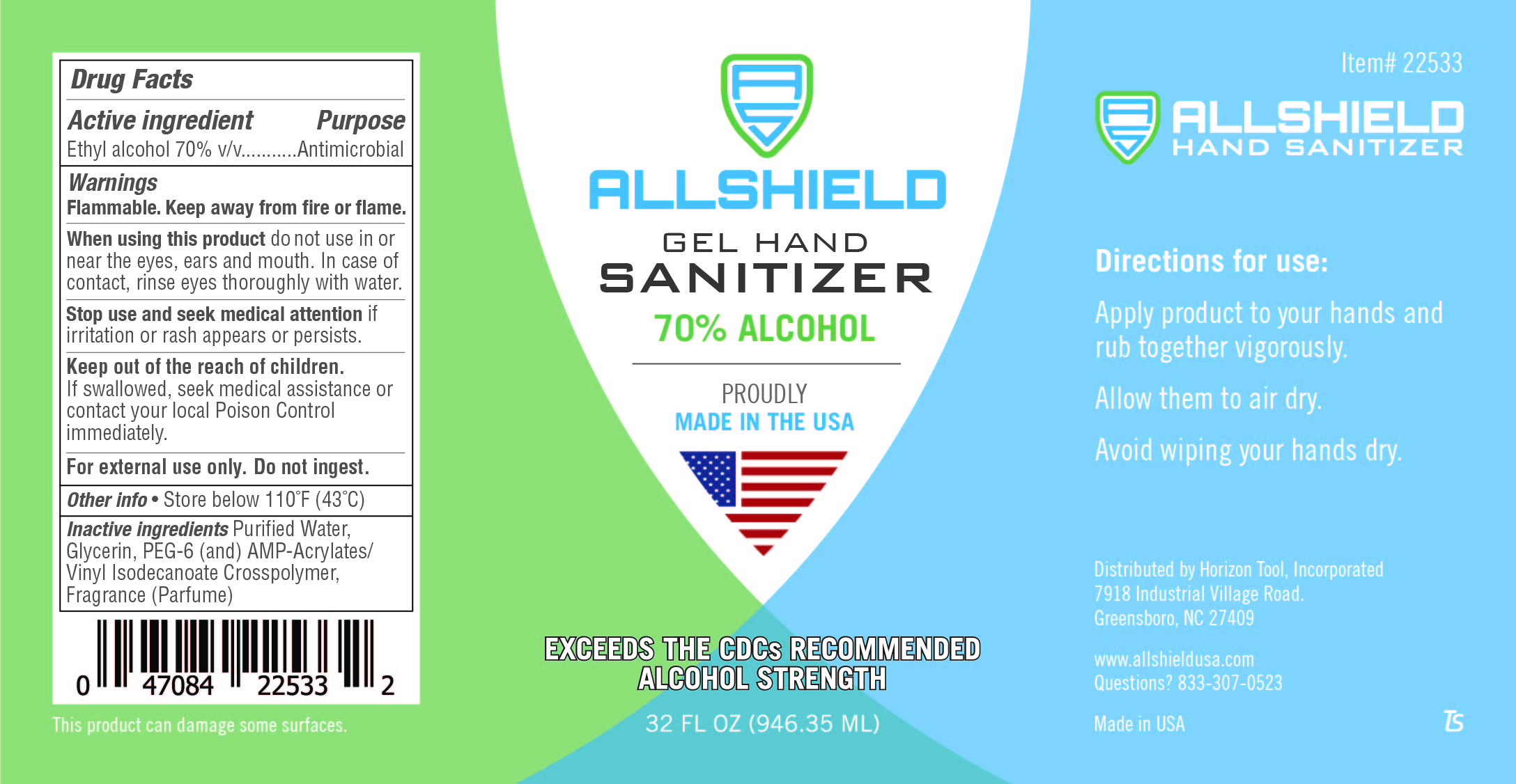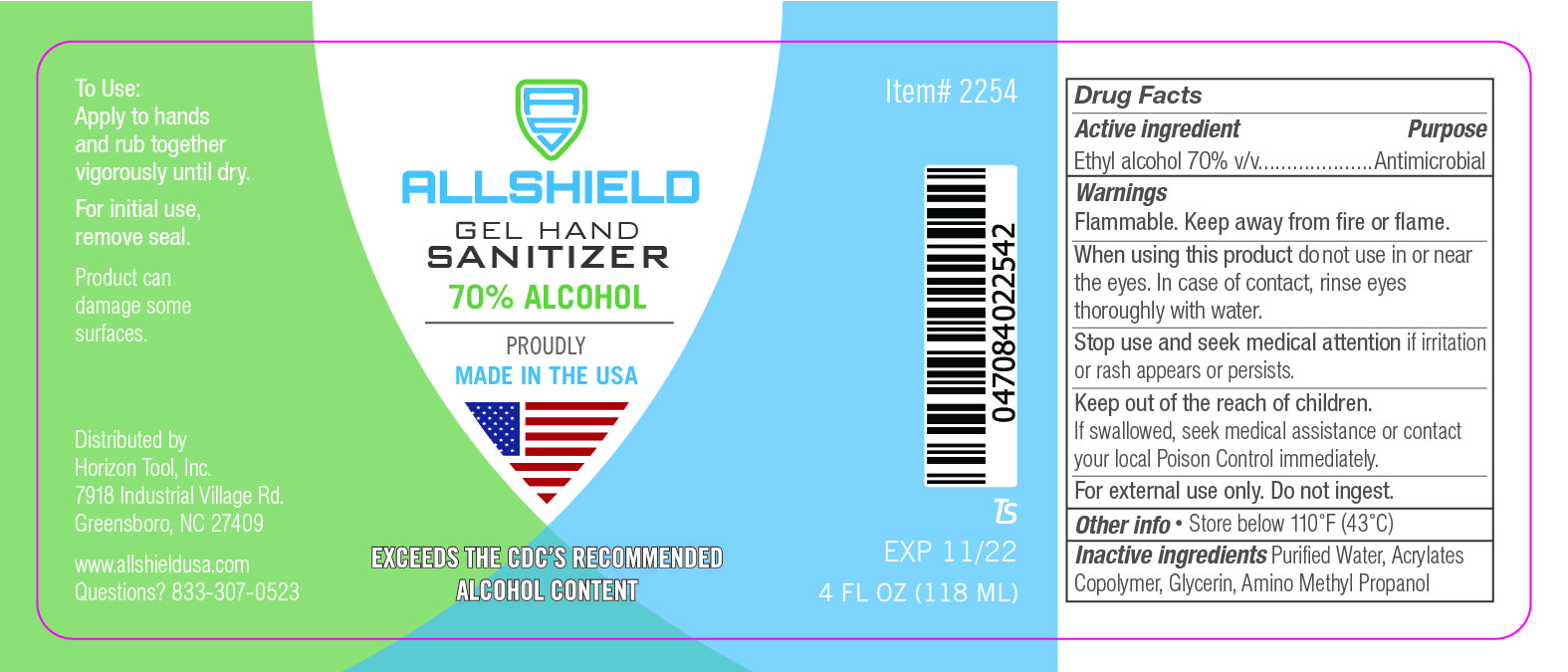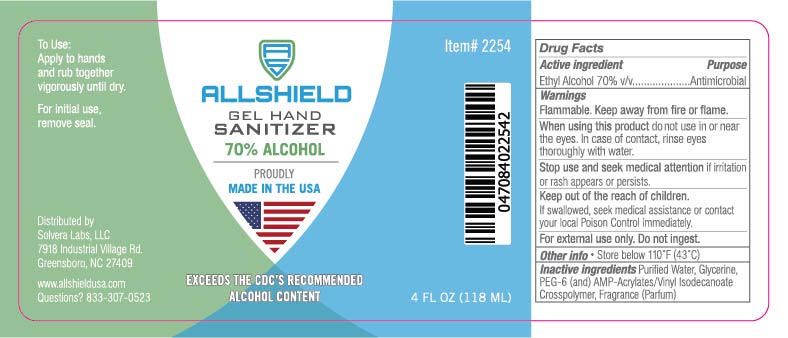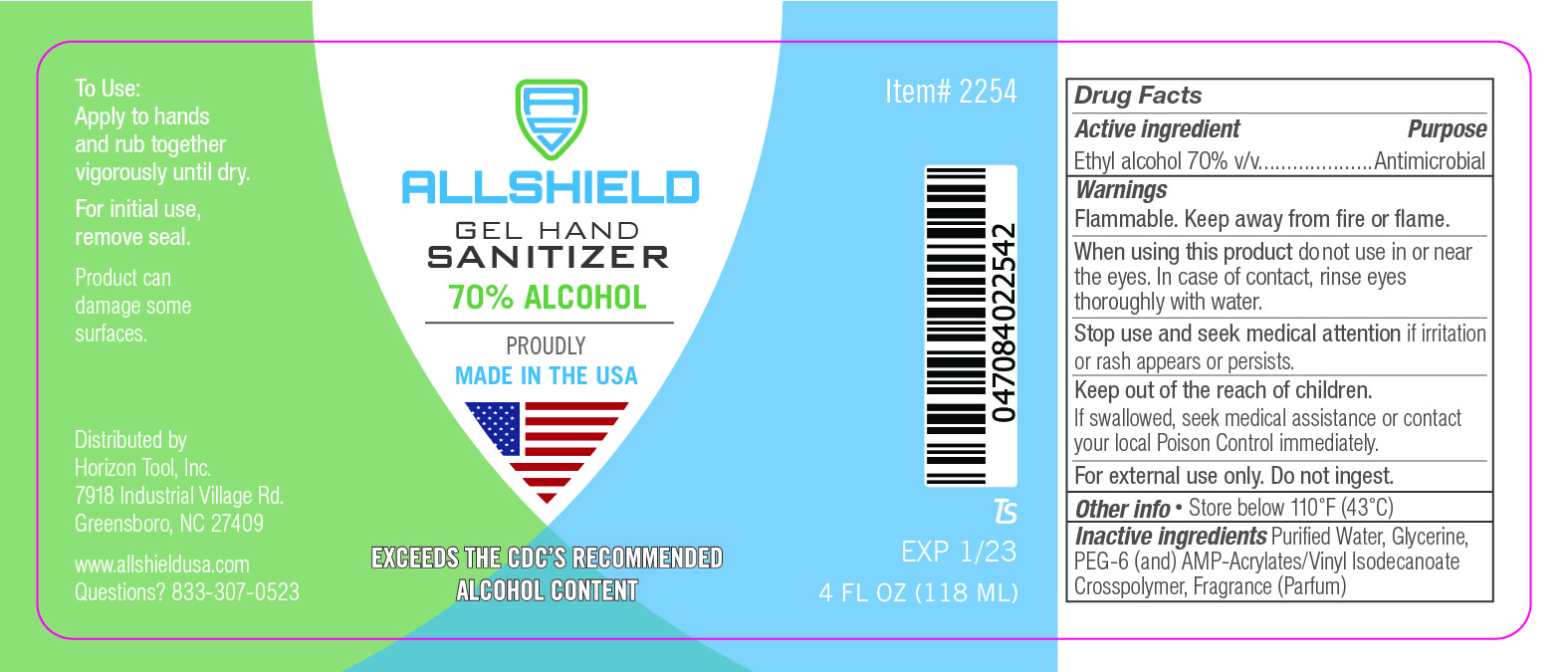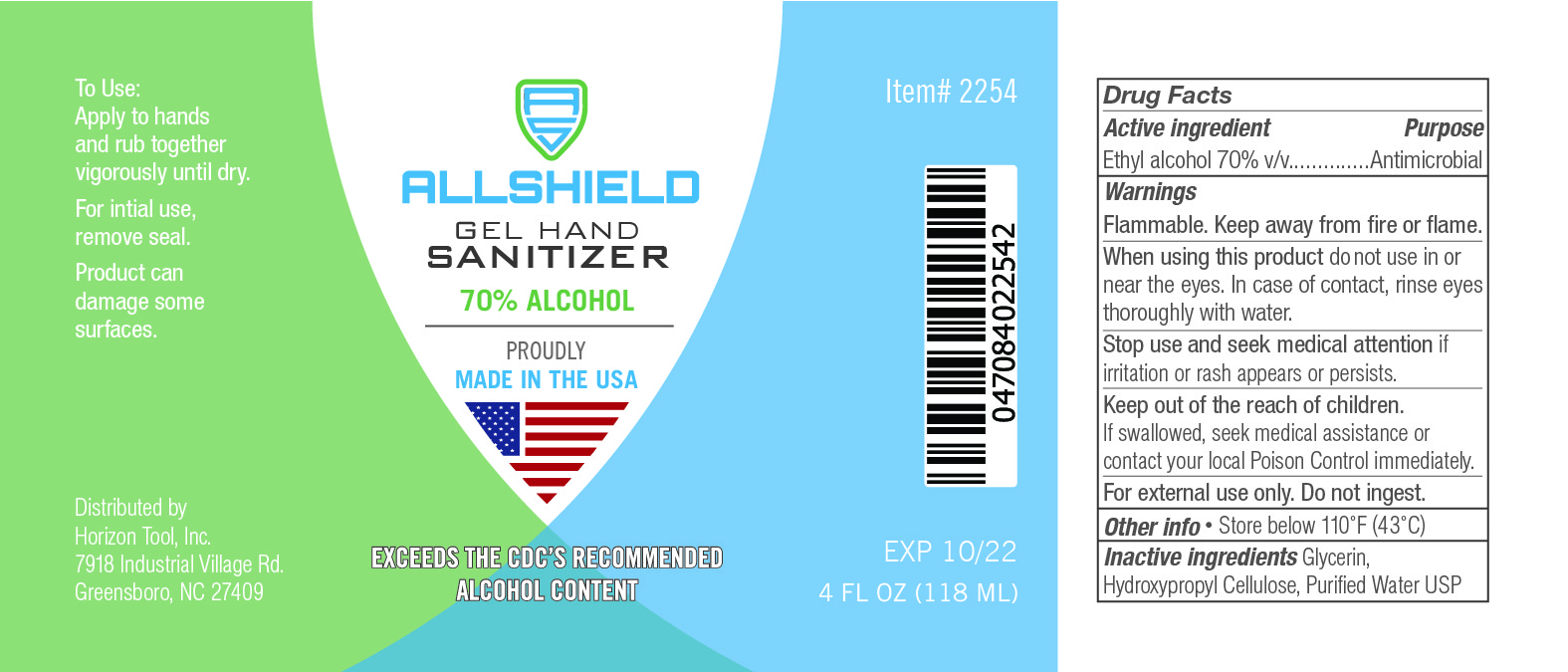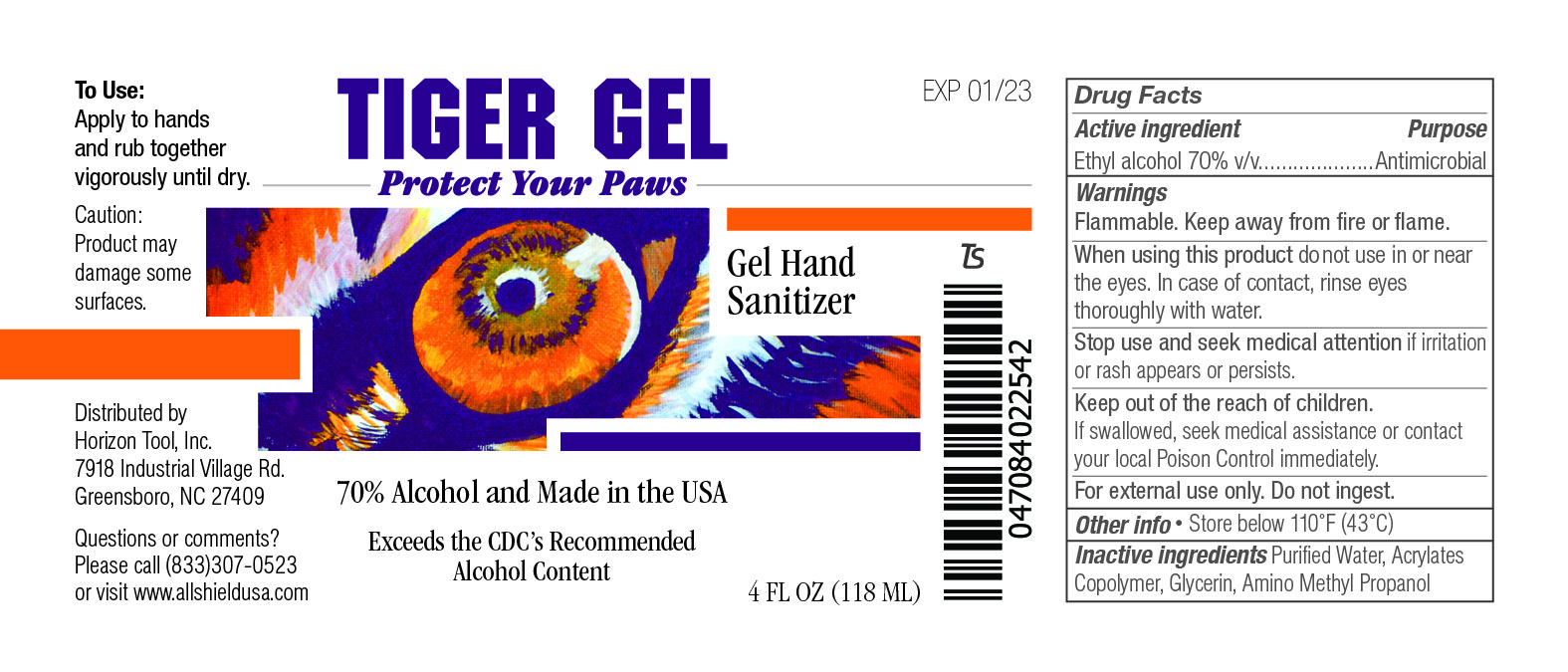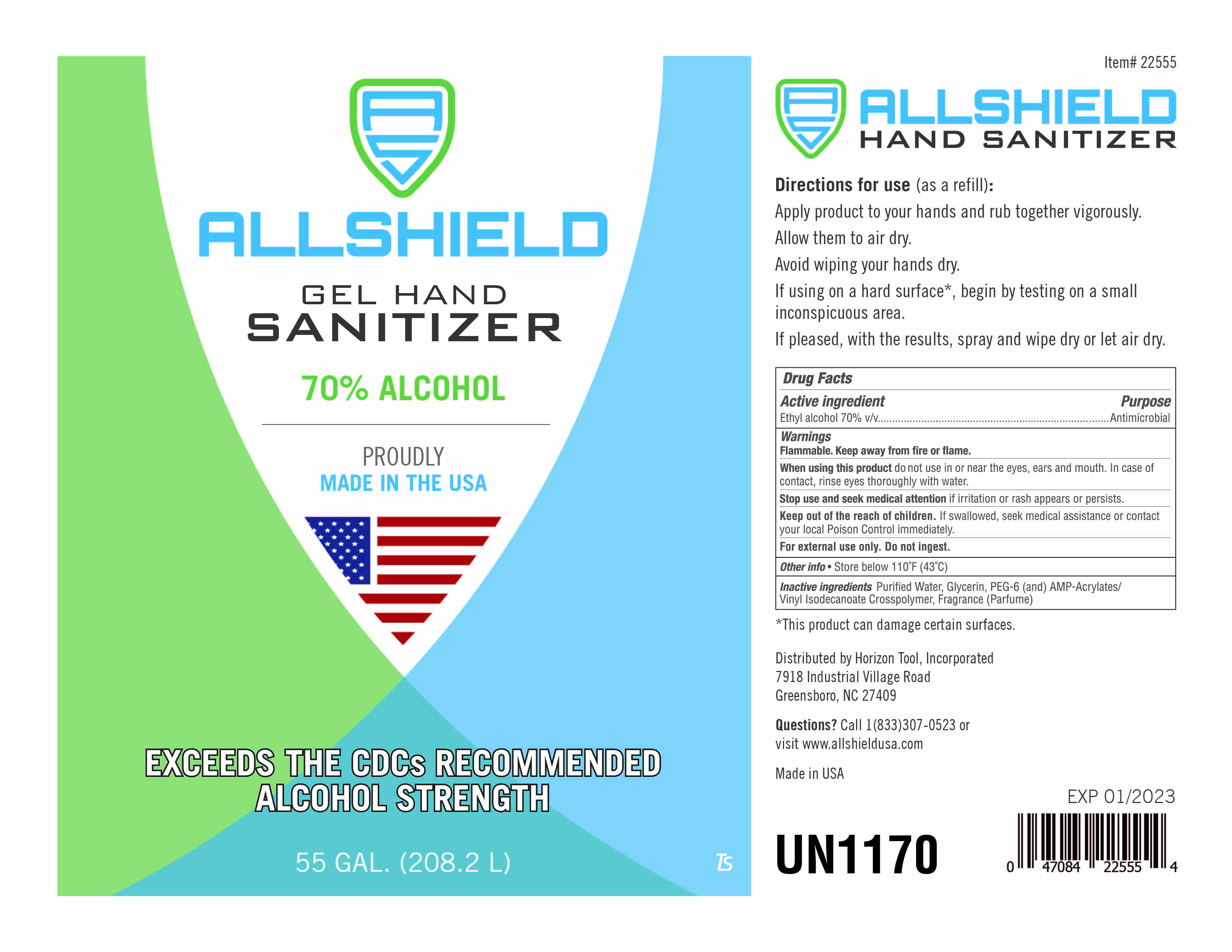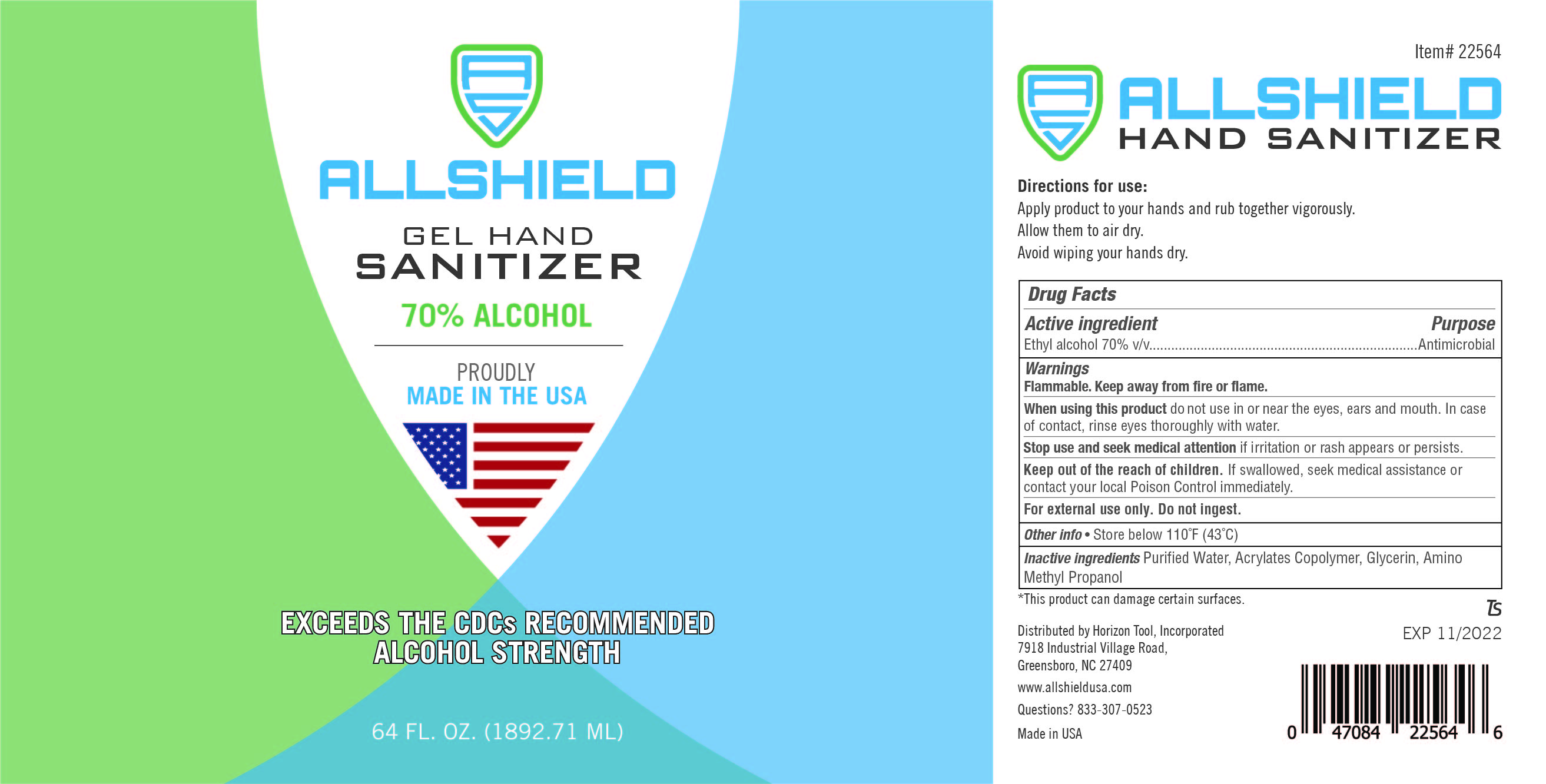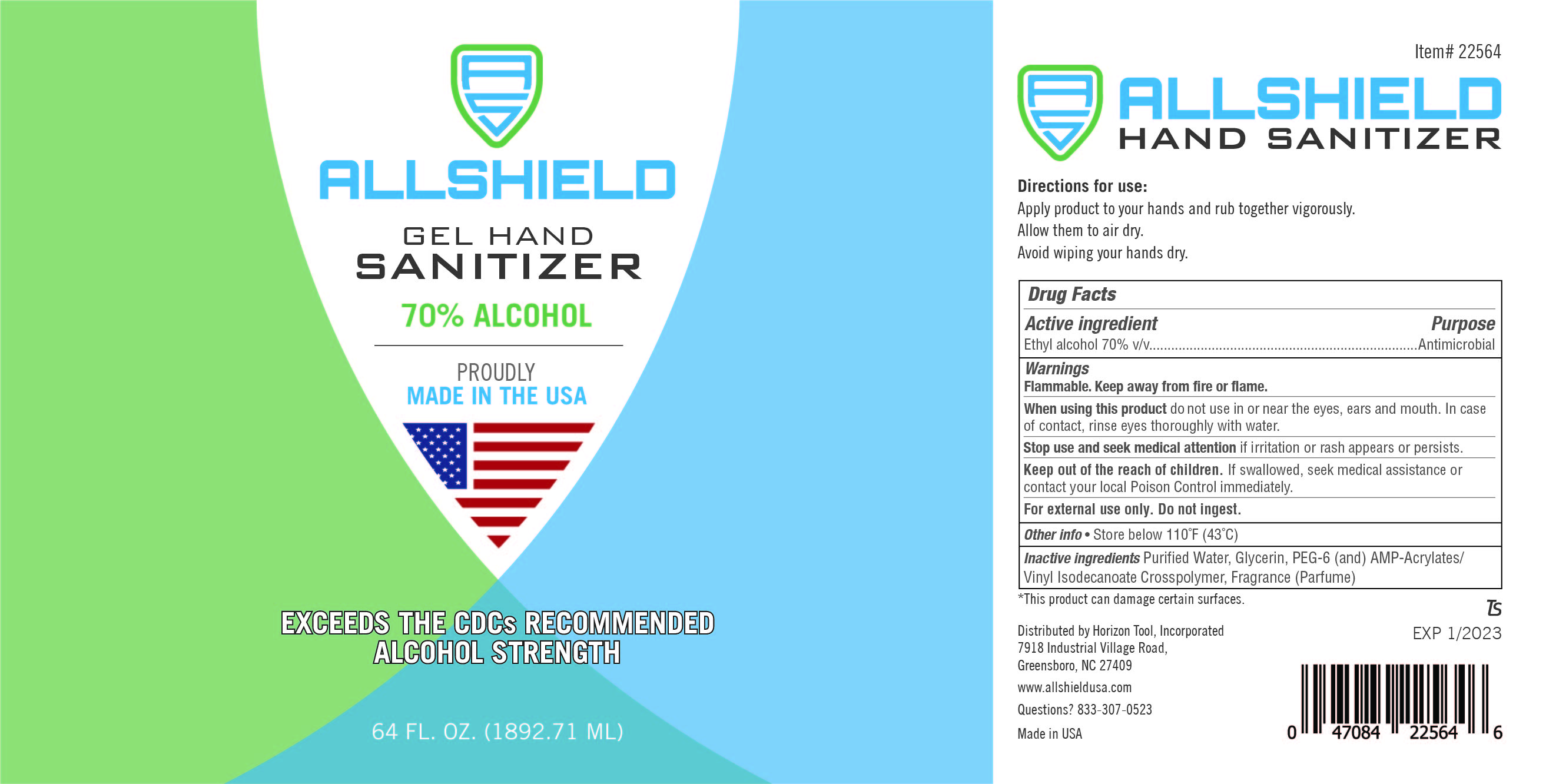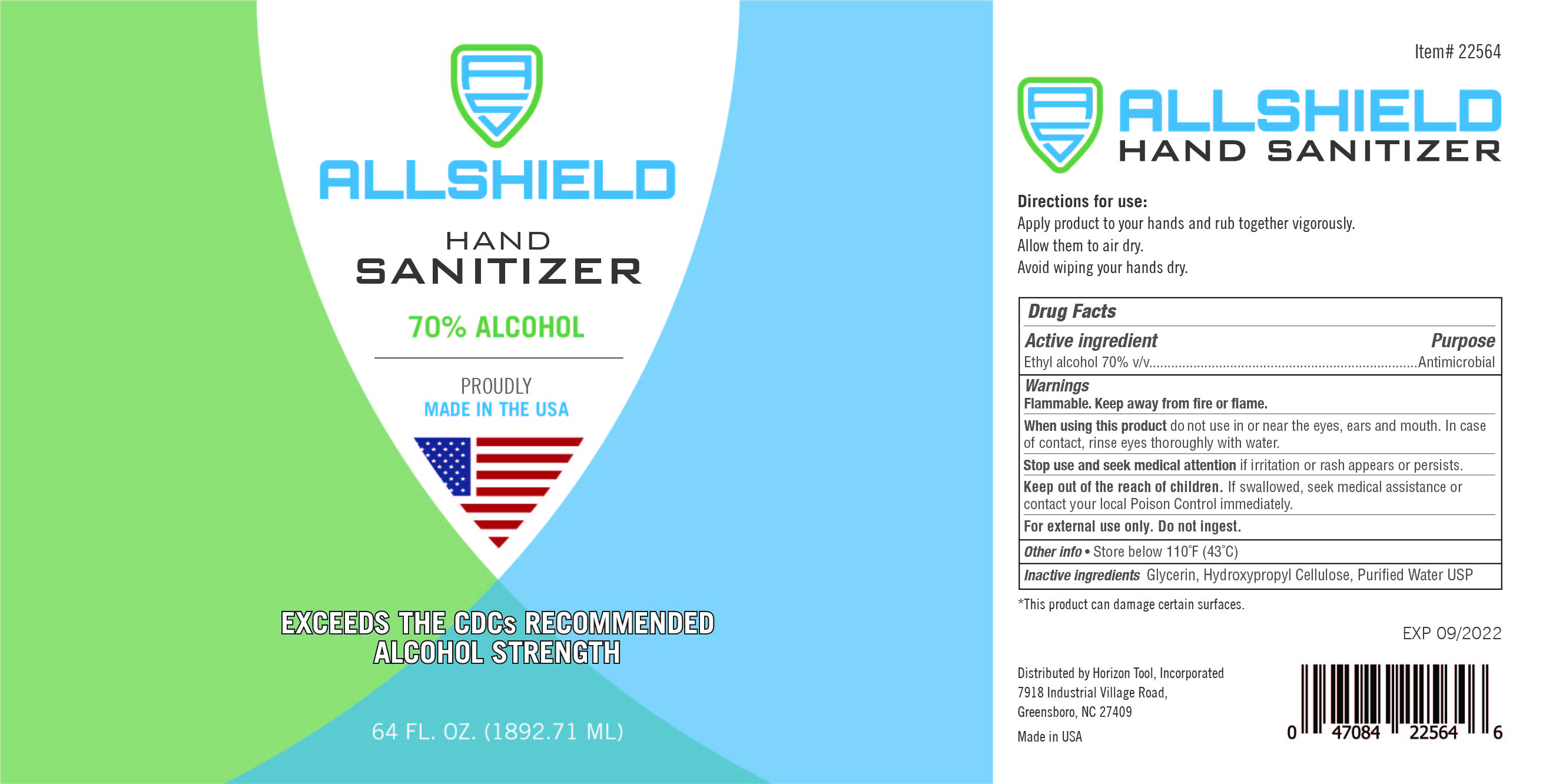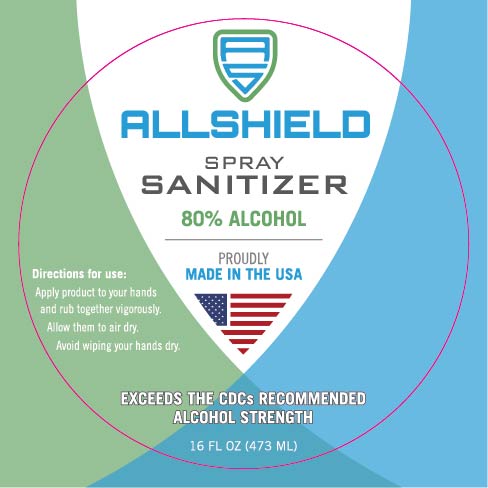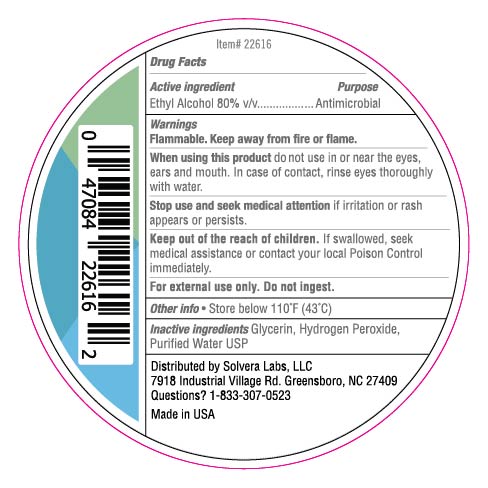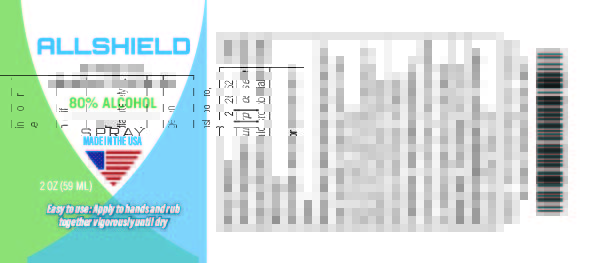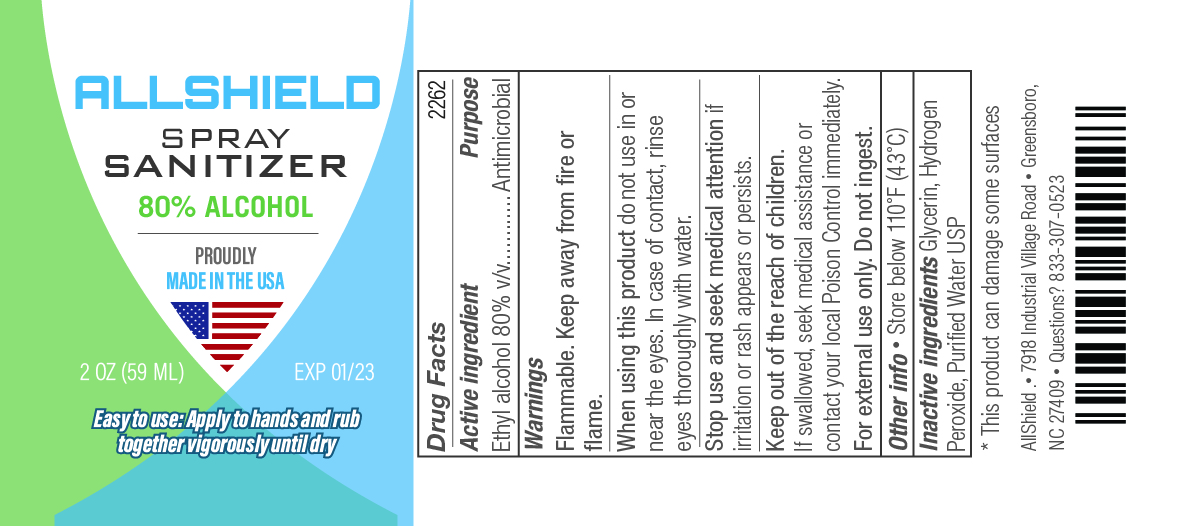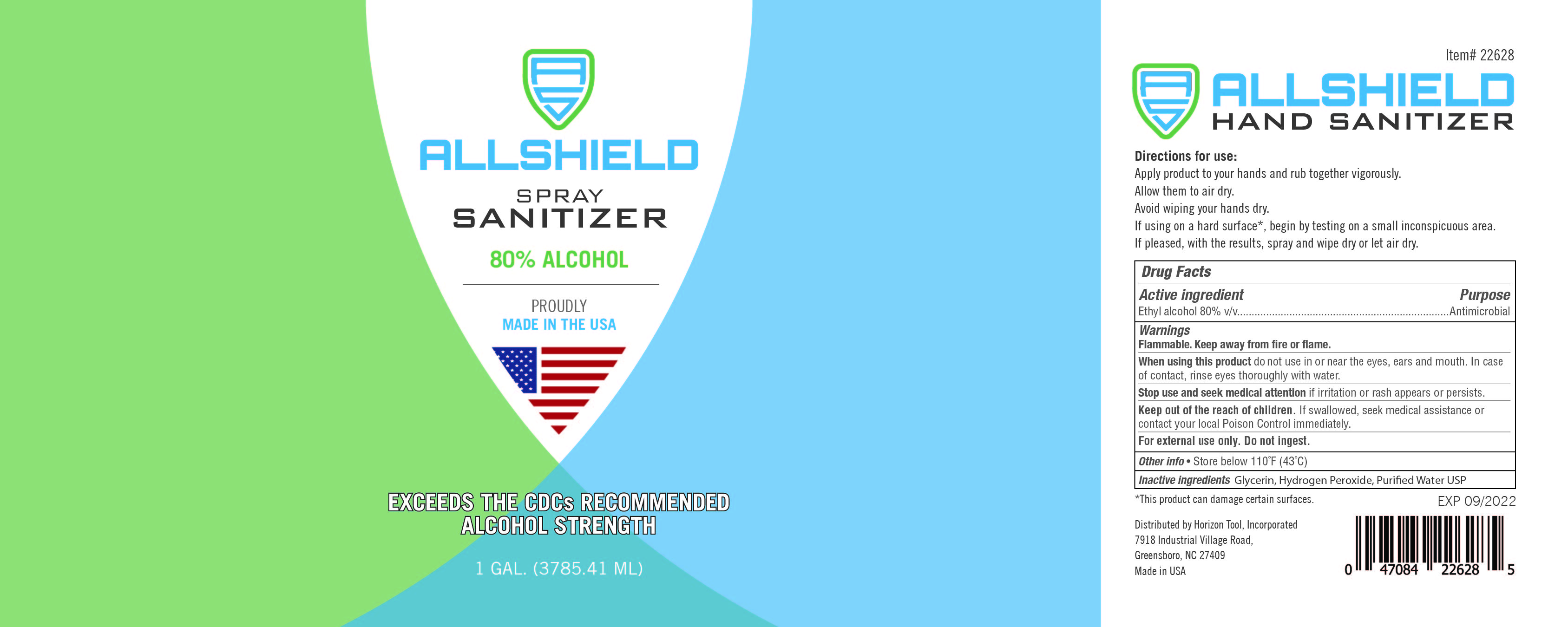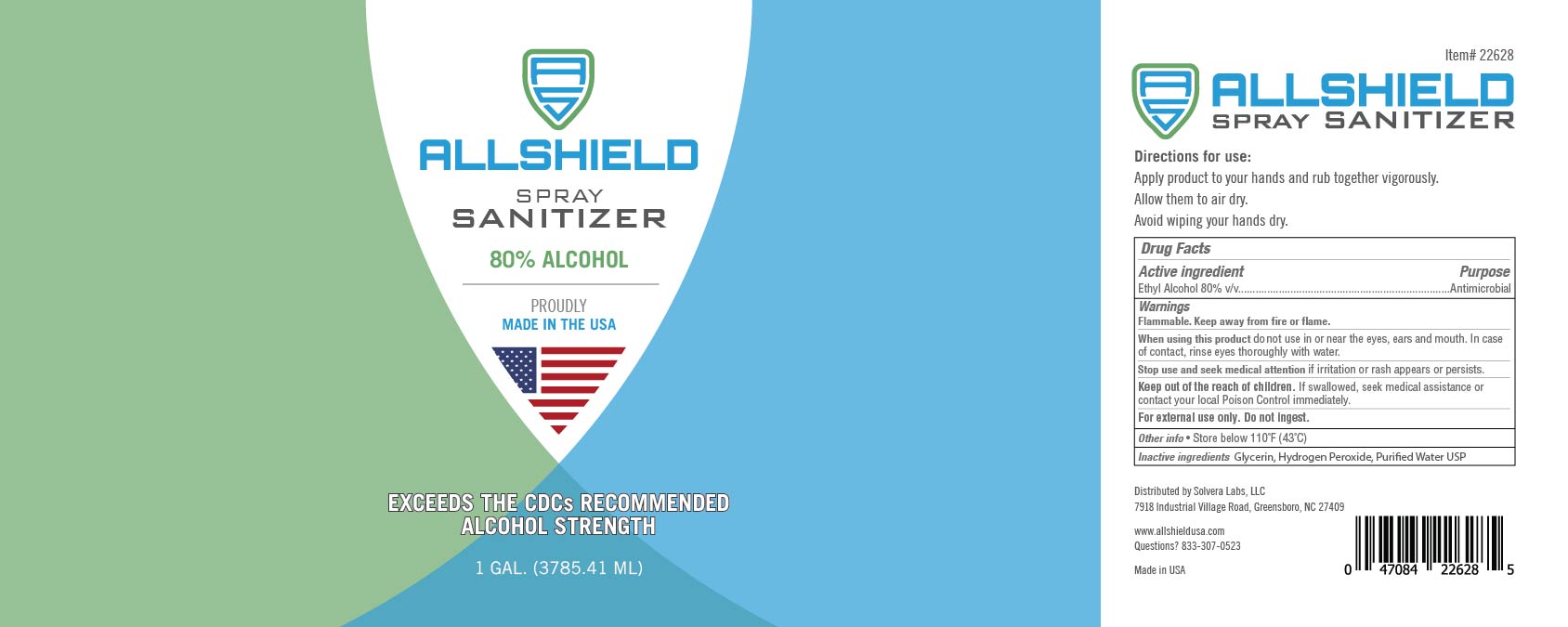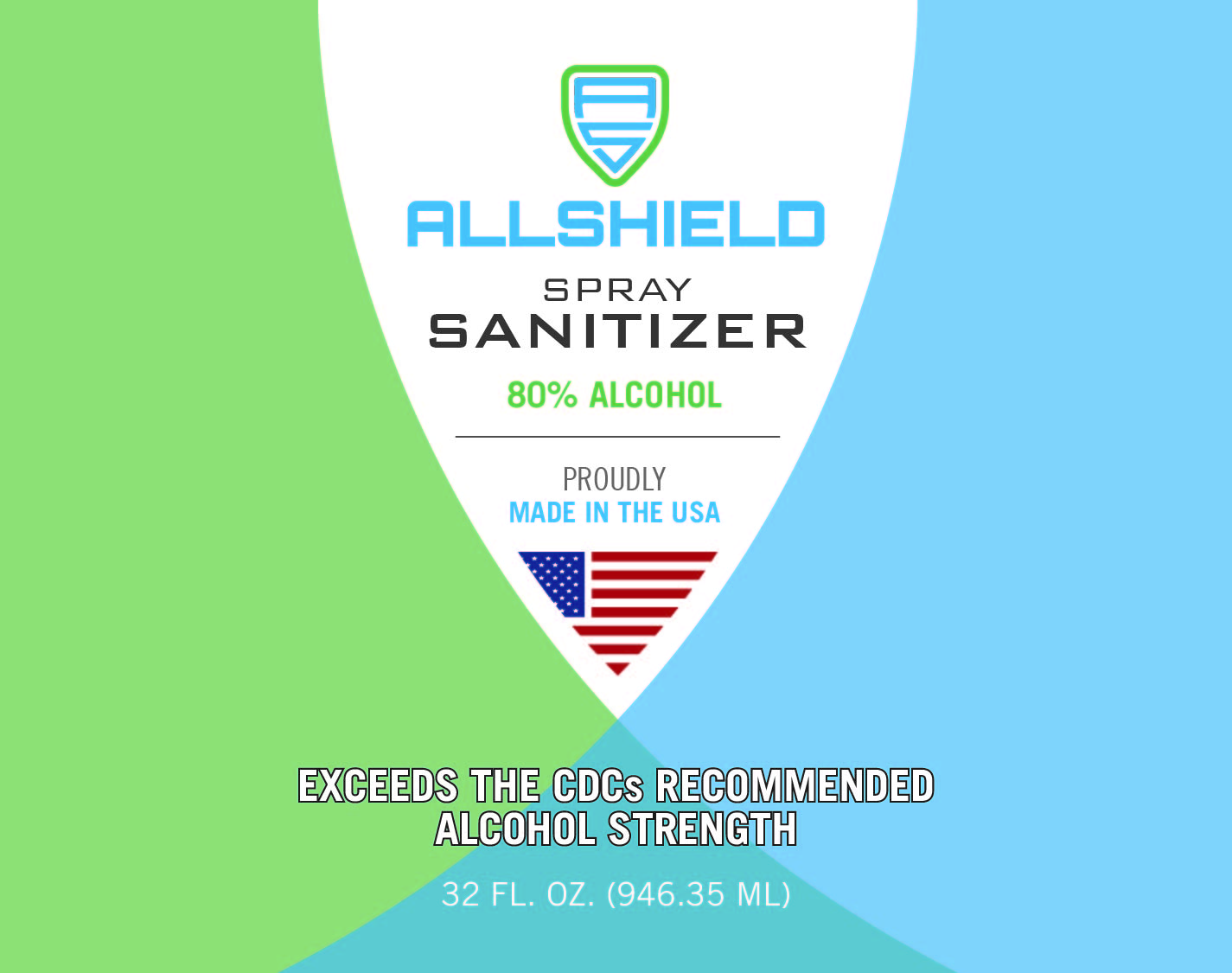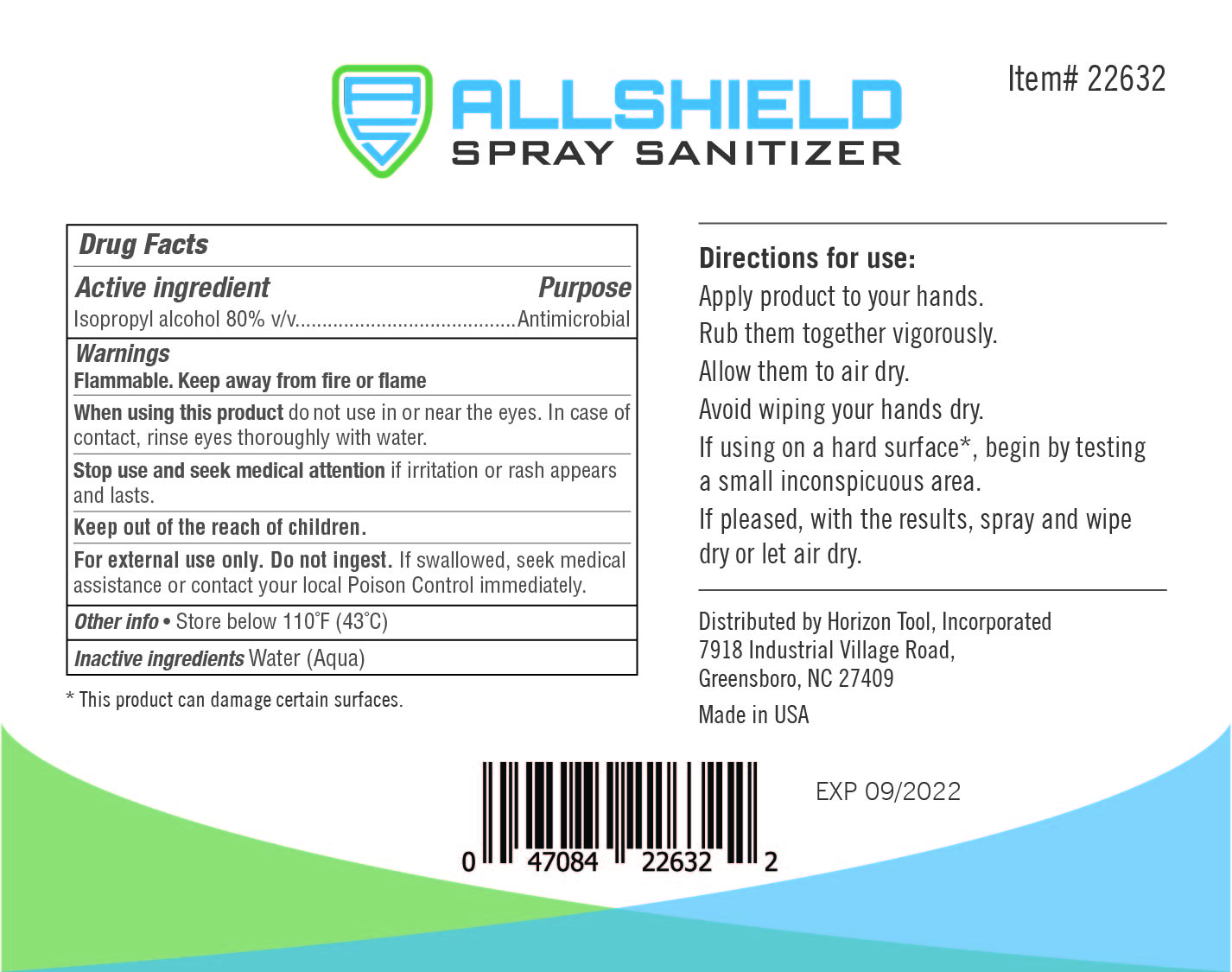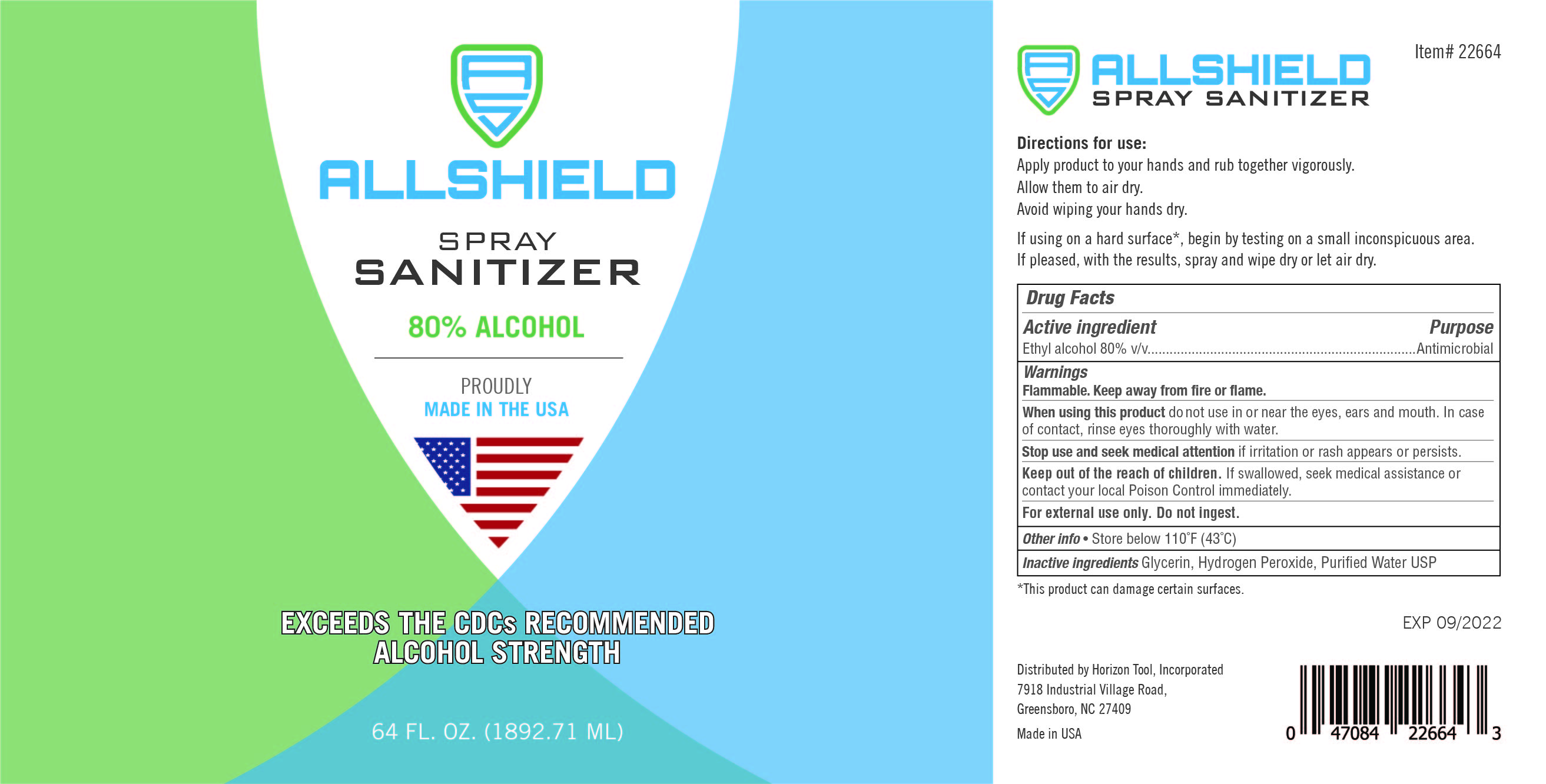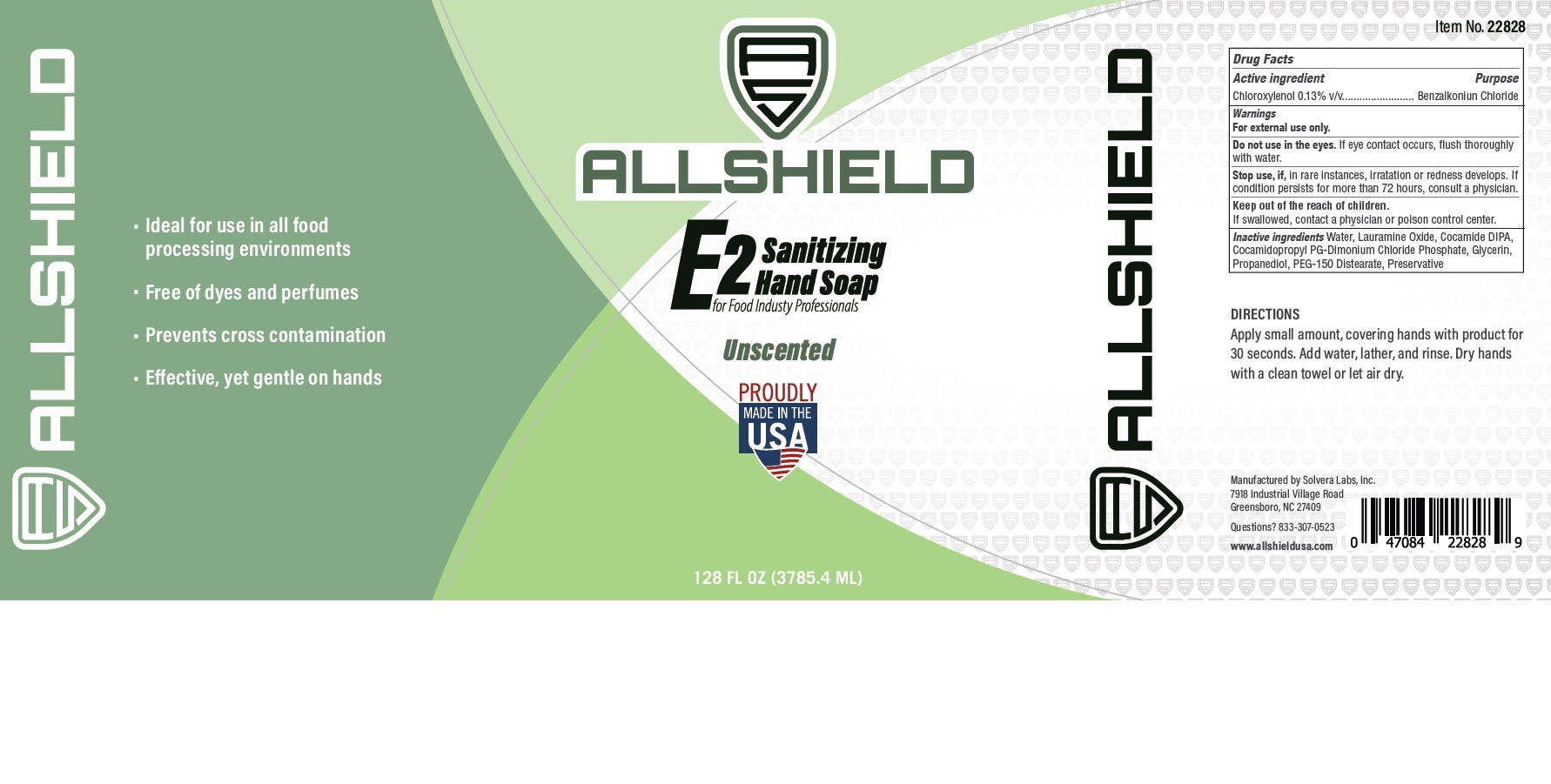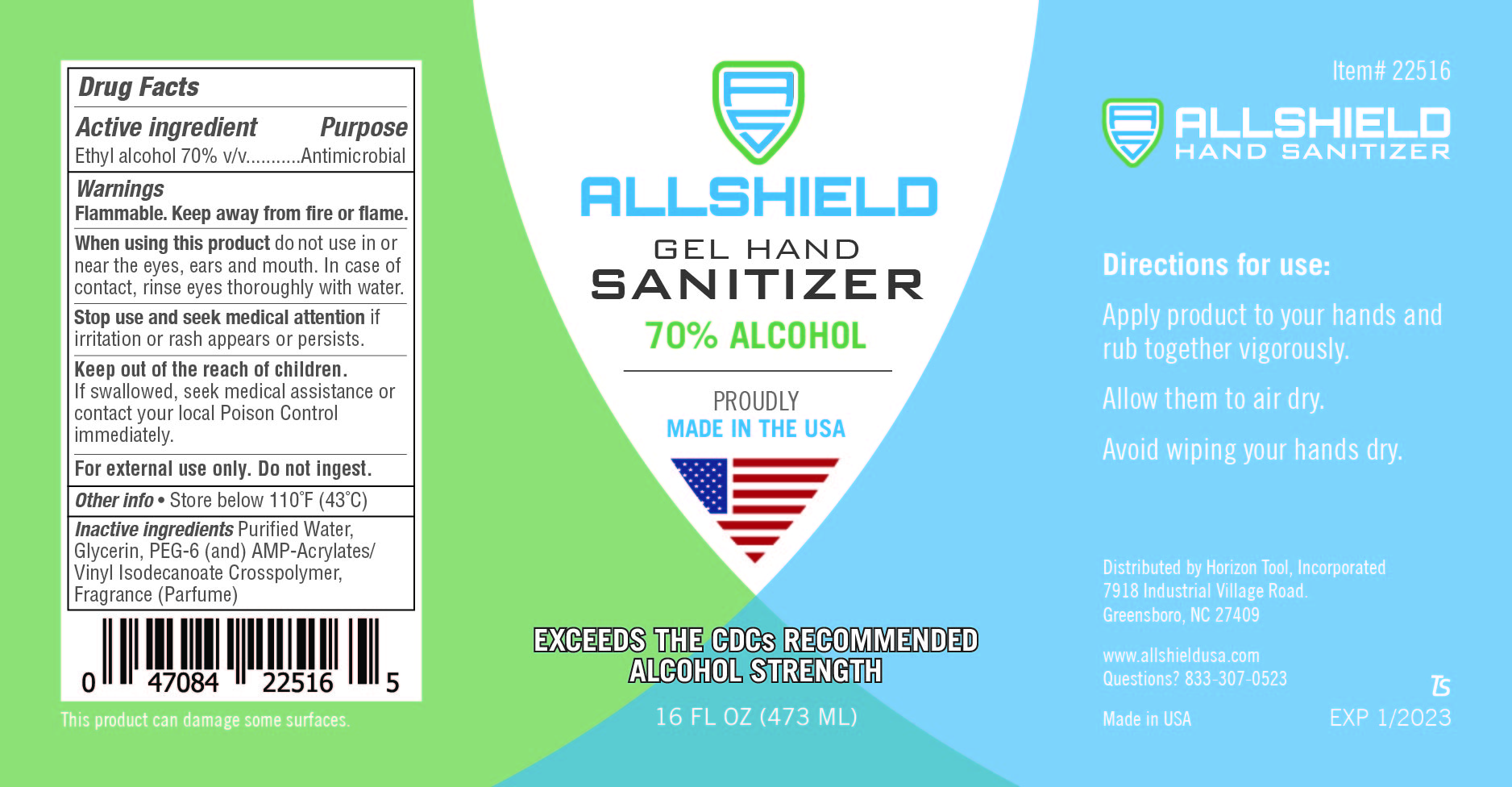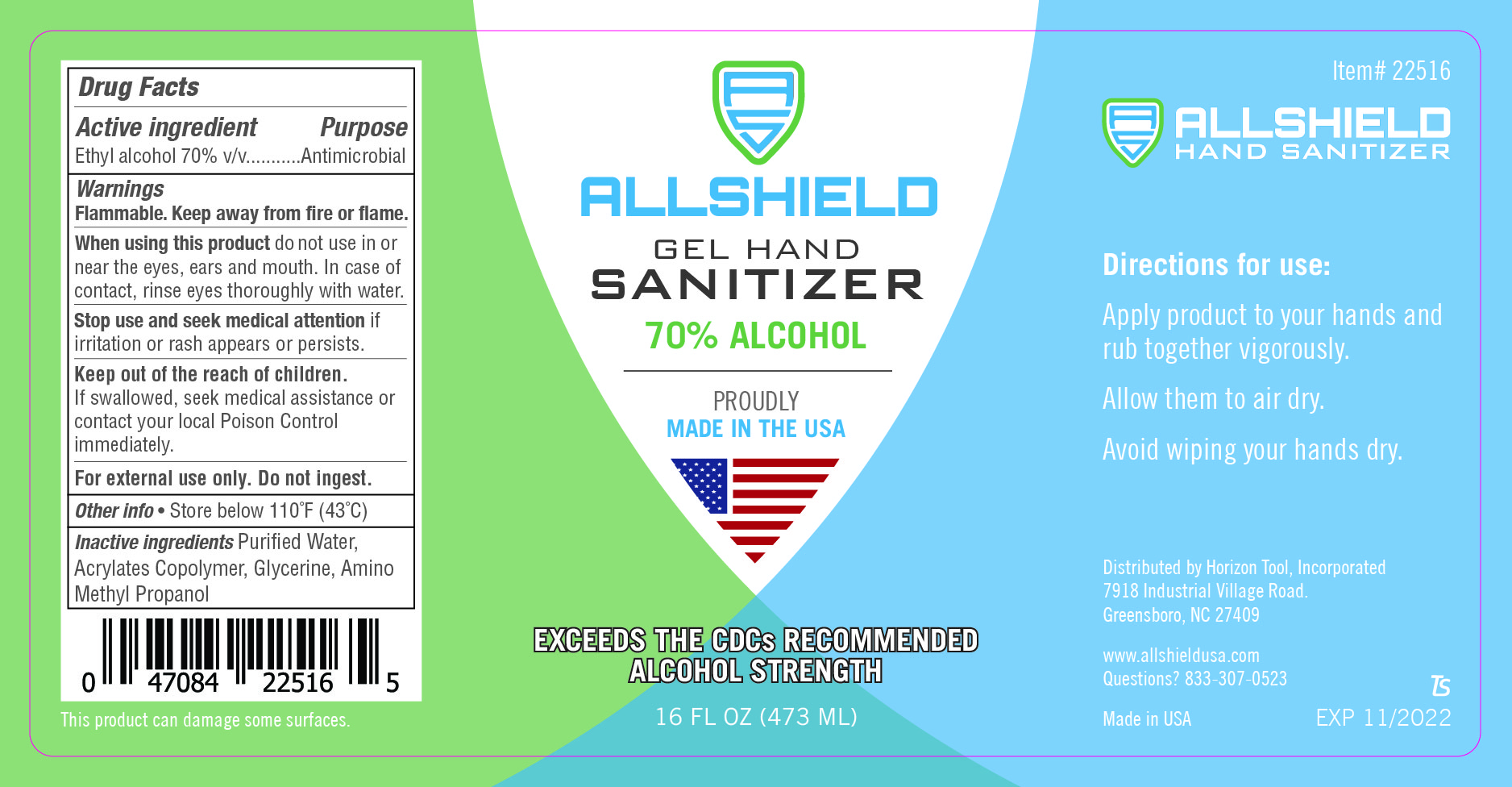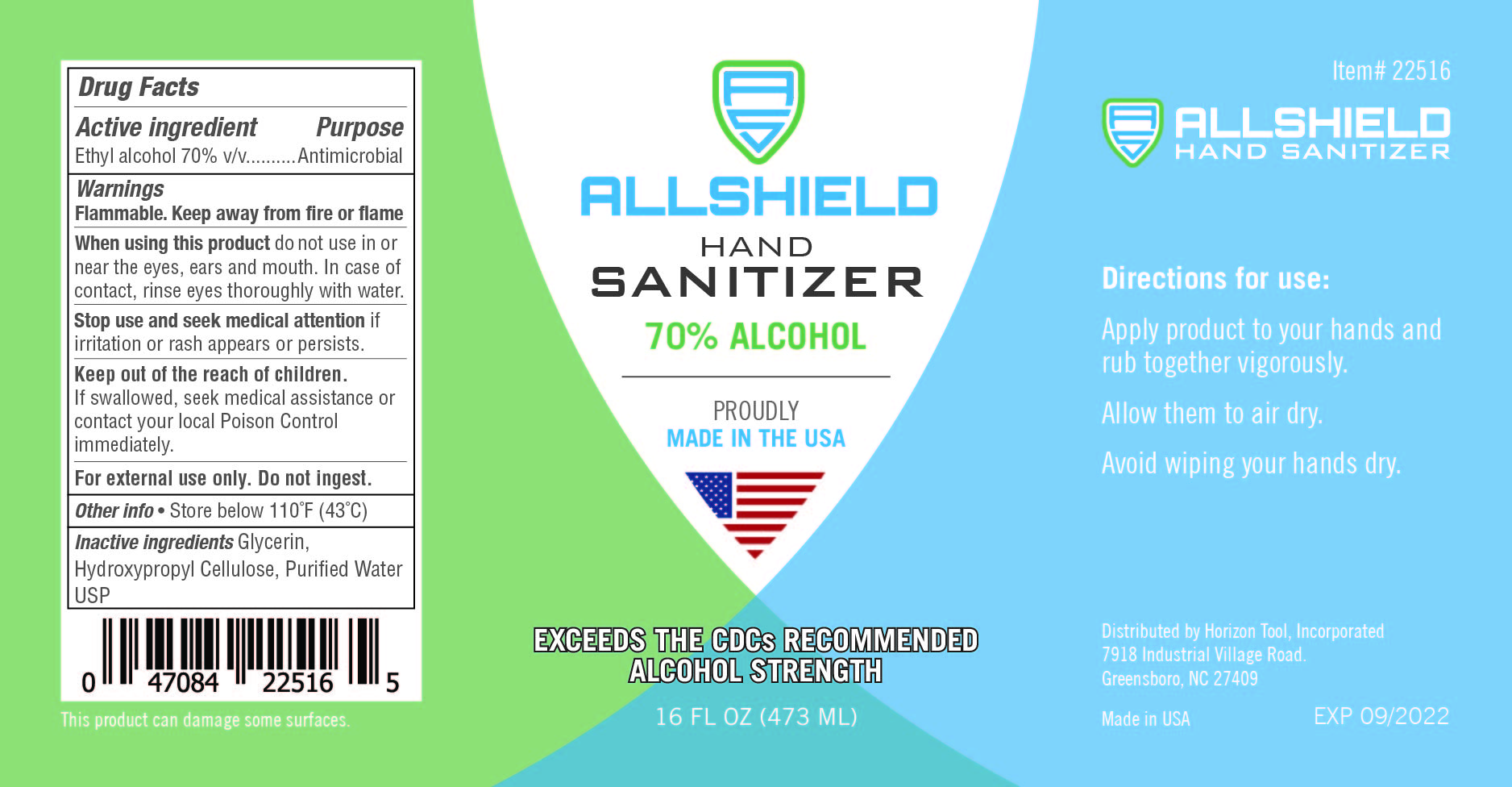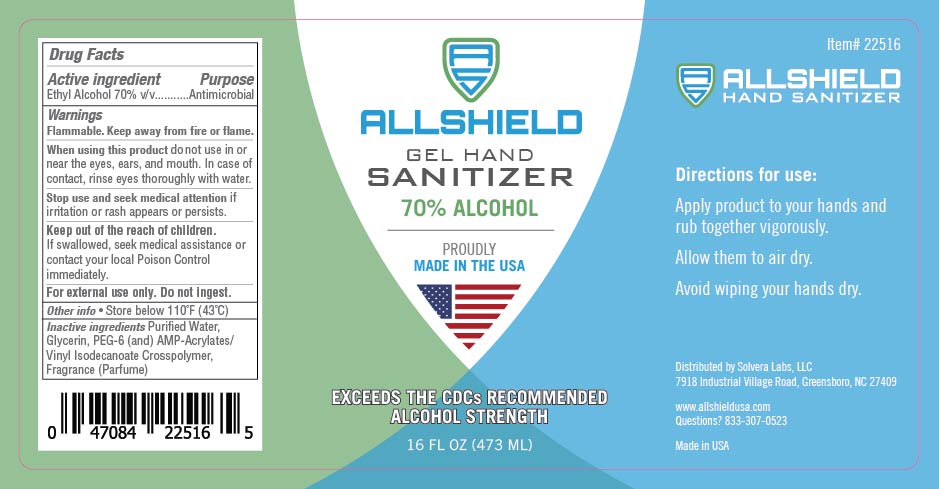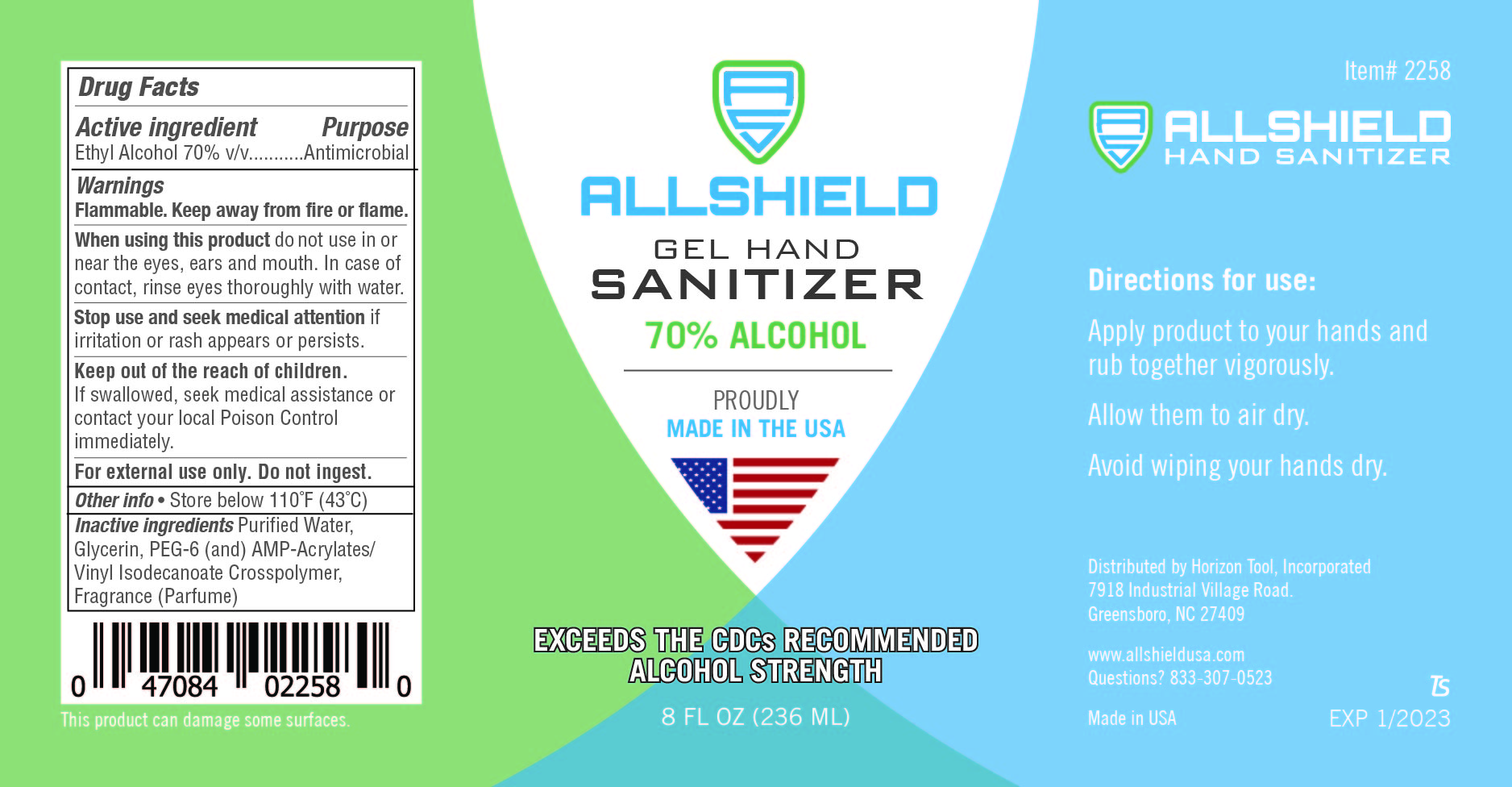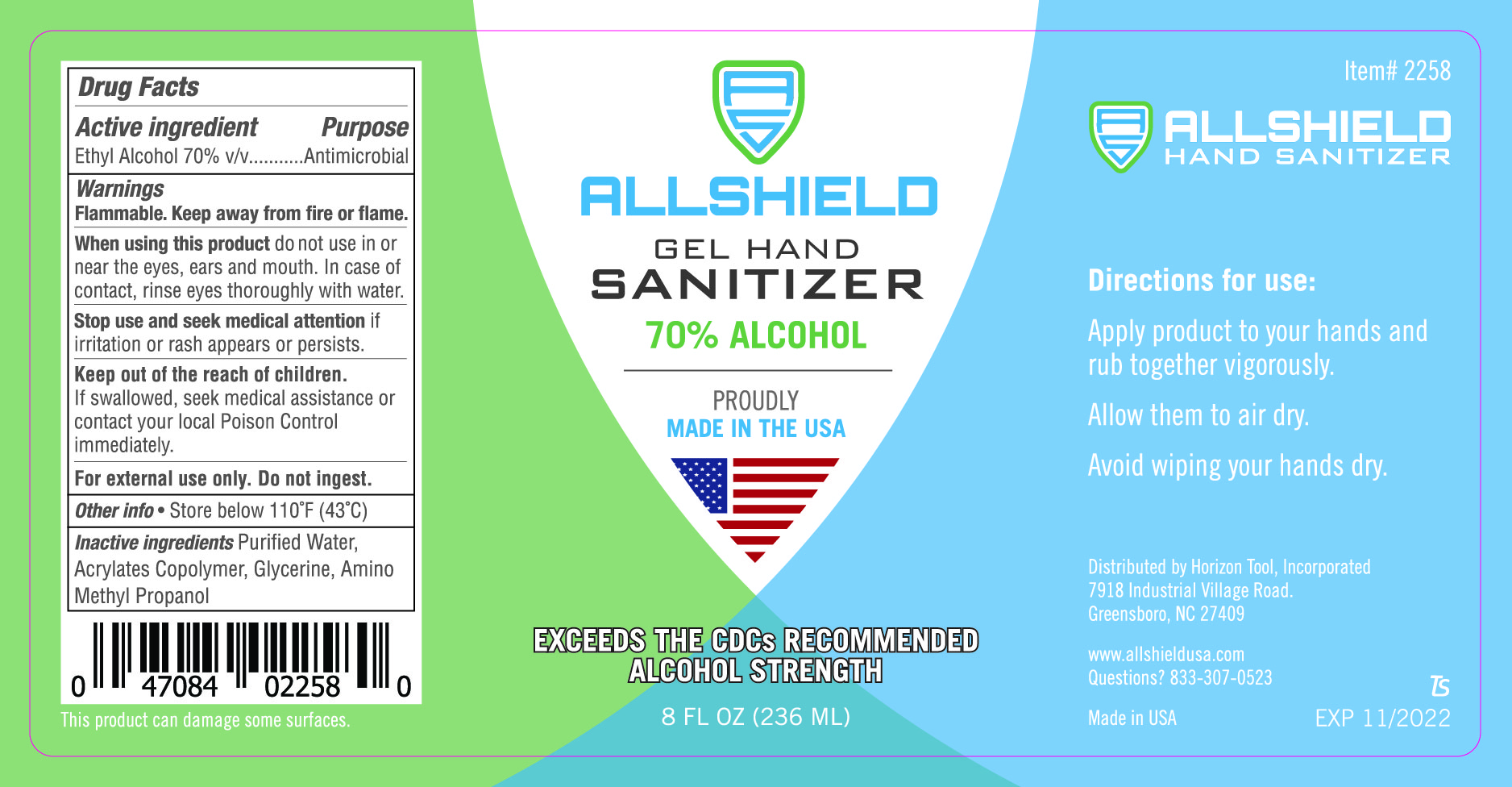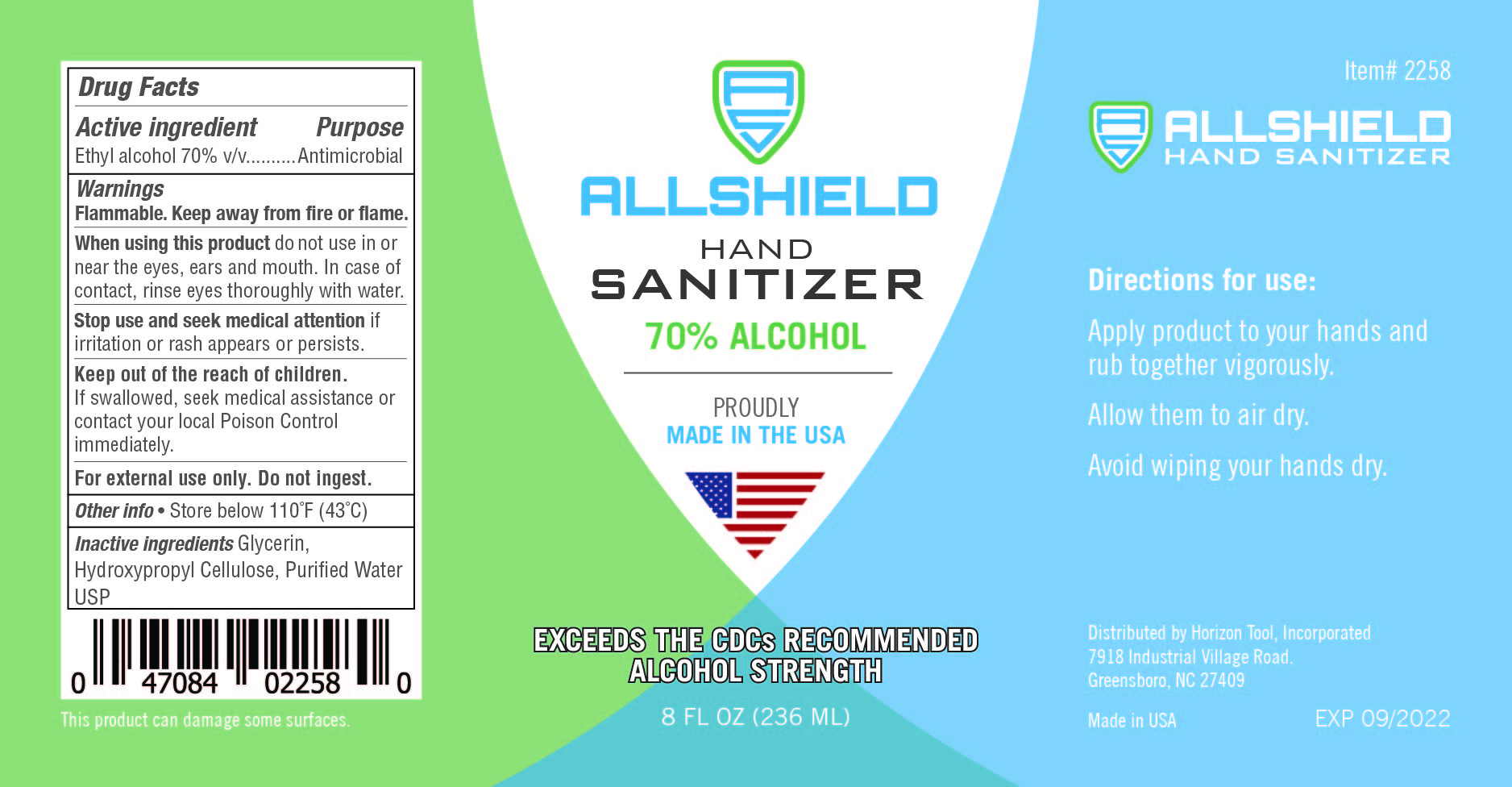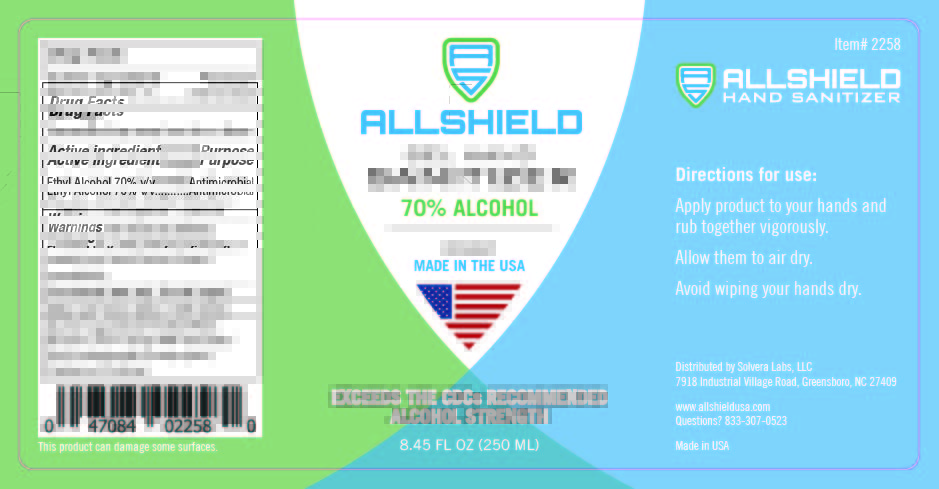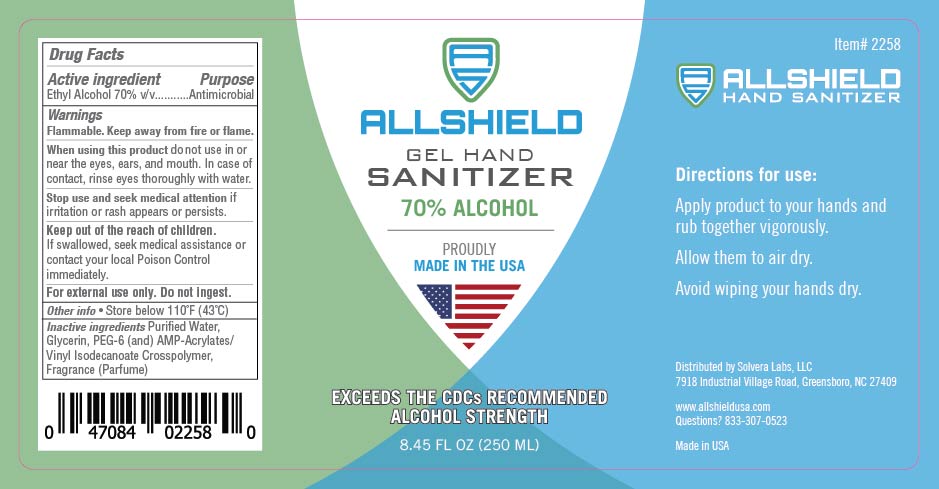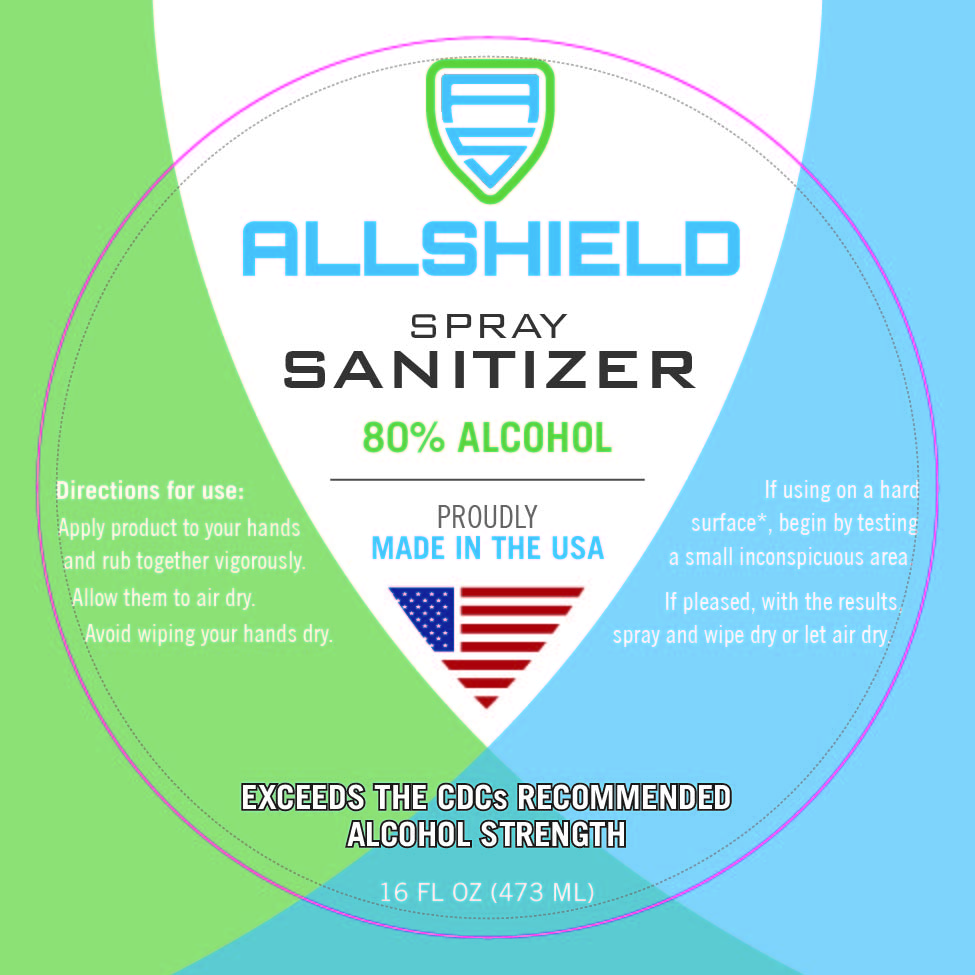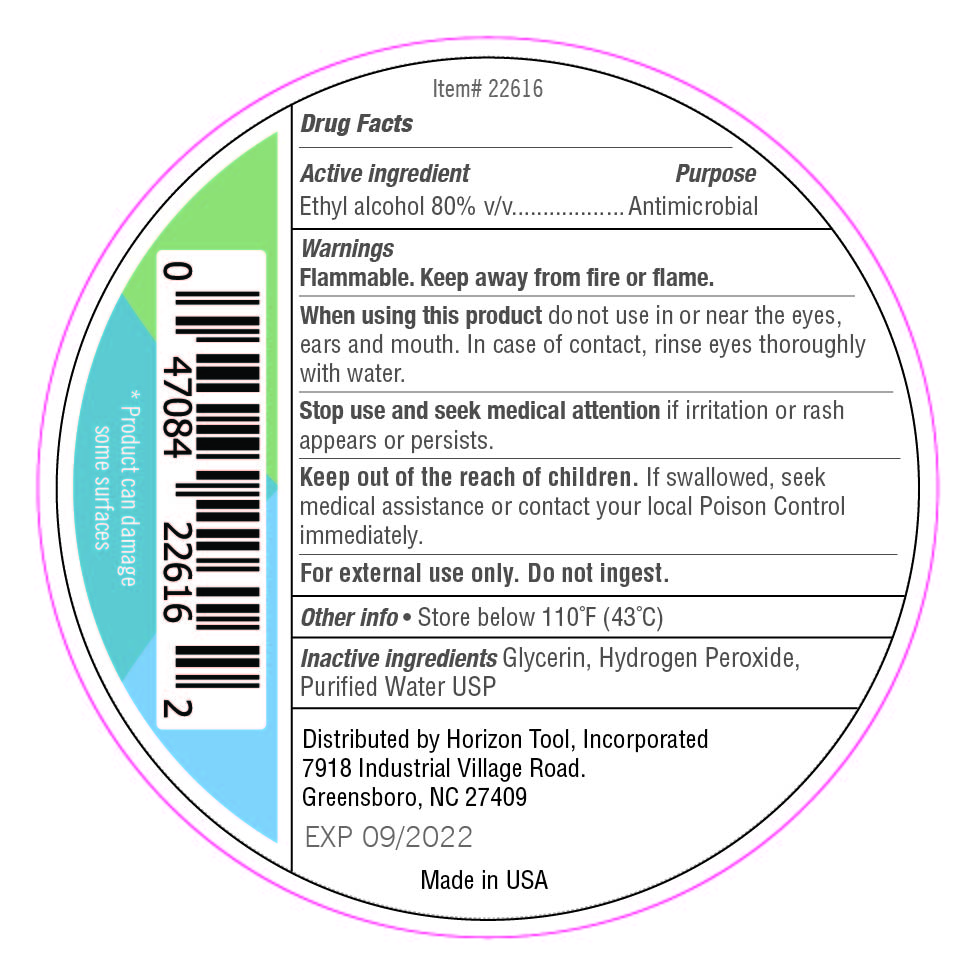 DRUG LABEL: E2 hand wash
NDC: 74683-6200 | Form: SOAP
Manufacturer: Horizon Tool Inc.
Category: otc | Type: HUMAN OTC DRUG LABEL
Date: 20250606

ACTIVE INGREDIENTS: BENZALKONIUM CHLORIDE 0.13 mg/100 mL
INACTIVE INGREDIENTS: COCAMIDOPROPYL BETAINE 1.4 mL/100 mL; WATER 87.6 mL/100 mL; ANHYDROUS CITRIC ACID 0.0004 mL/100 mL; METHYLCHLOROISOTHIAZOLINONE/METHYLISOTHIAZOLINONE MIXTURE 0.07 mL/100 mL; SODIUM CHLORIDE 1.4 mL/100 mL; SODIUM LAURYL SULFATE 4 mL/100 mL; COCO DIETHANOLAMIDE 1.1 mL/100 mL; SODIUM LAURETH SULFATE 4.2 mL/100 mL

This is a hand sanitizer manufactured according to the Temporary Policy for Preparation of Certain Alcohol-Based Hand Sanitizer Products During the Public Health Emergency (CoViD-19); Guidance for Industry.

The hand sanitizer is manufactured using only the following United States Pharmacopoeia (USP) grade ingredients in the preparation of the product (percentage in final product formulation) consistent with World Health Organization (WHO) recommendations:

1. Alcohol (ethanol) (USP or Food Chemical Codex (FCC) grade) (80%, volume/volume (v/v)) in an aqueous solution denatured according to Alcohol and Tobacco Tax and Trade Bureau regulations in 27 CFR part 20.
2. Glycerol (1.45% v/v).
3. Hydrogen peroxide (0.125% v/v).
4. Sterile distilled water or boiled cold water.

The firm does not add other active or inactive ingredients. Different or additional ingredients may impact the quality and potency of the product.

Active Ingredient(s)

Alcohol 80% v/v. Purpose: Antiseptic

Purpose

Antiseptic, Hand Sanitizer

Use

Hand Sanitizer to help reduce bacteria that potentially can cause disease. For use when soap and water are not available.

Warnings

For external use only. Flammable. Keep away from heat or flame

Do not use

- in children less than 2 months of age
- on open skin wounds

When using this product keep out of eyes, ears, and mouth. In case of contact with eyes, rinse eyes thoroughly with water.
Stop use and ask a doctor if irritation or rash occurs. These may be signs of a serious condition.
Keep out of reach of children. If swallowed, get medical help or contact a Poison Control Center right away.

Stop use and ask a doctor if irritation or rash occurs. These may be signs of a serious condition.

Keep out of reach of children. If swallowed, get medical help or contact a Poison Control Center right away.

Directions

- Place enough product on hands to cover all surfaces. Rub hands together until dry.
- Supervise children under 6 years of age when using this product to avoid swallowing.

Other information

- Store between 15-30C (59-86F)
- Avoid freezing and excessive heat above 40C (104F)

Inactive ingredients

glycerin, hydrogen peroxide, purified water USP

Package Label - Principal Display Panel

3785.5 mL NDC: 74683-6400-1

3785.4 mL NDC: 74683-6300-1

3785.41 mL NDC: 74683-2001-2

473 mL NDC: 74683-2001-1

118 mL NDC: 74683-5001-4

250 mL NDC: 74683-5001-3

59 mL NDC: 74683-5001-2

473 mL NDC: 74683-5001-1

250 mL NDC: 74683-1002-1

3785.4 mL NDC: 74683-6200-3

250 mL NDC: 7463-6200-2

3785.4 mL NDC: 74683-6200-1

3785.4 mL NDC: 74683-6000-1

59 mL NDC: 74683-2100-1

946.35 mL NDC: 74683-3001-1

262 mL NDC: 74683-2500-1

1892.71 mL NDC: 74683-5000-9

208.2 L NDC: 74683-5000-8

946.35 mL NDC: 74683-5000-7

946.35 mL NDC: 74683-5000-7

473 mL NDC: 74683-5000-6

3785.41 mL NDC: 74683-5000-5

3785.41 mL NDC: 74683-5000-4

354.8 mL NDC: 74683-5000-3

236 mL NDC: 74683-5000-2

118 mL NDC: 74683-5000-1

118 mL NDC: 74683-4000-1

3 mL NDC 74683-3000-8

3 mL NDC 74683-3000-8

3 mL NDC 74683-3000-9

3 mL NDC 74683-3000-9

3785.41 mL NDC 74683-3000-7

3785.41 mL NDC 74683-3000-6

3785.41 mL NDC 74683-3000-5

1892.71 mL NDC 74683-3000-4

946.35 mL NDC 74683-3000-3

946.35 mL NDC 74683-3000-3

118 mL NDC 74683-3000-2

59 mL NDC 74683-3000-1

59 mL NDC 74683-3000-1

473 mL NDC 74683-1000-9

236 mL NDC 74683-1000-8

059 mL NDC: 74683-1000-6

059 mL NDC: 74683-1000-6

74683-1000-7

236 mL NDC: 74683-2000-1 473 mL NDC: 74683-1000-2

946.35 mL NDC: 74683-1000-3 946.35 mL NDC: 74683-1000-3

1892.71 mL NDC: 74683-1000-4

3785.41 mL NDC: 74683-1000-5

473 mL NDC: 74683-2000-1

473 mL NDC: 74683-2000-1

946.35 mL NDC: 74683-2000-2

946.35 mL NDC: 74683-2000-2

1892.71 mL NDC: 74683-2000-3

3785.41 mL NDC: 74683-2000-4